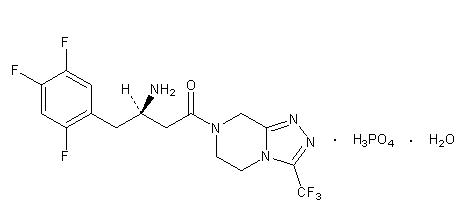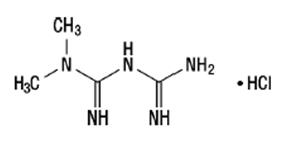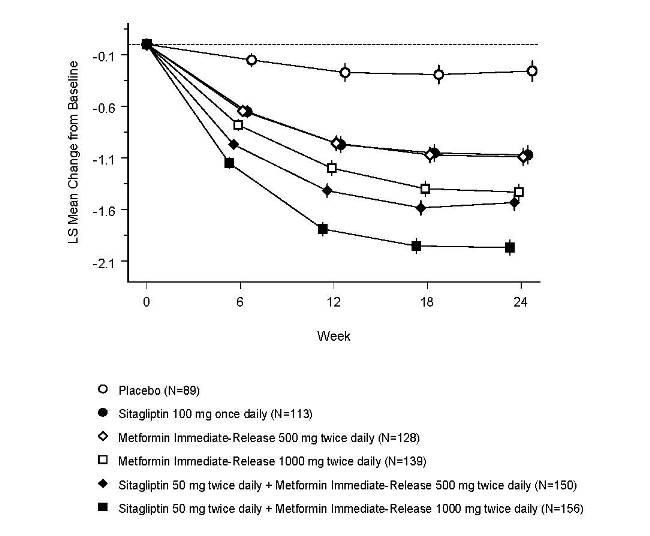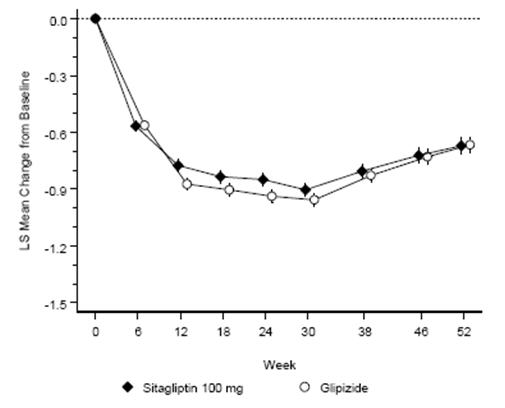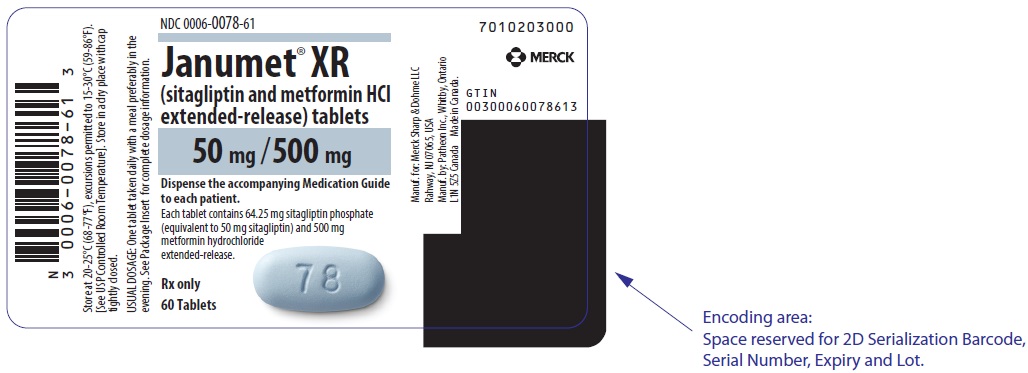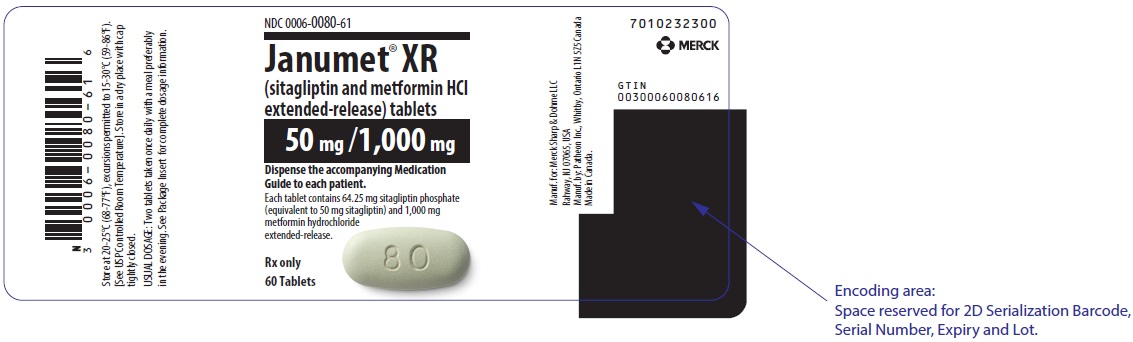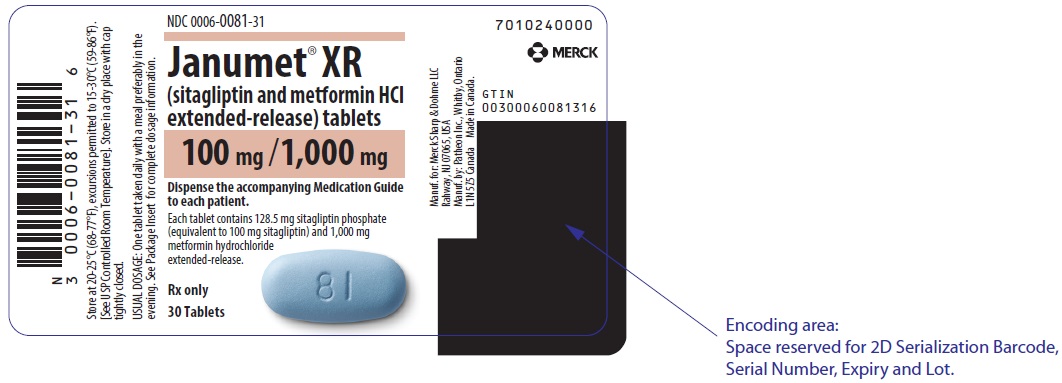 DRUG LABEL: JANUMET 
NDC: 0006-0078 | Form: TABLET, FILM COATED, EXTENDED RELEASE
Manufacturer: Merck Sharp & Dohme LLC
Category: prescription | Type: HUMAN PRESCRIPTION DRUG LABEL
Date: 20250325

ACTIVE INGREDIENTS: SITAGLIPTIN PHOSPHATE 50 mg/1 1; METFORMIN HYDROCHLORIDE 500 mg/1 1
INACTIVE INGREDIENTS: POVIDONE K30; HYPROMELLOSE 2208 (100000 MPA.S); SILICON DIOXIDE; SODIUM STEARYL FUMARATE; PROPYL GALLATE; POLYETHYLENE GLYCOL 3350; KAOLIN; HYPROMELLOSE 2910 (6 MPA.S); HYDROXYPROPYL CELLULOSE (1600000 WAMW); TITANIUM DIOXIDE; FD&C BLUE NO. 2; INDIGOTINDISULFONATE SODIUM; ALUMINUM OXIDE; CARNAUBA WAX; MICROCRYSTALLINE CELLULOSE

HIGHLIGHTS OF PRESCRIBING INFORMATION

These highlights do not include all the information needed to use JANUMET XR safely and effectively. See full prescribing information for JANUMET XR.
JANUMET® XR (sitagliptin and metformin hydrochloride extended-release) tablets, for oral use
Initial U.S. Approval: 2012

WARNING: LACTIC ACIDOSIS

See full prescribing information for complete boxed warning.

- Postmarketing cases of metformin-associated lactic acidosis have resulted in death, hypothermia, hypotension, and resistant bradyarrhythmias. Symptoms included malaise, myalgias, respiratory distress, somnolence, and abdominal pain. Laboratory abnormalities included elevated blood lactate levels, anion gap acidosis, increased lactate/pyruvate ratio, and metformin plasma levels generally >5 mcg/mL. (5.1)
- Risk factors include renal impairment, concomitant use of certain drugs, age ≥65 years old, radiological studies with contrast, surgery and other procedures, hypoxic states, excessive alcohol intake, and hepatic impairment. Steps to reduce the risk of and manage metformin-associated lactic acidosis in these highrisk groups are provided in the Full Prescribing Information. (5.1)
- If lactic acidosis is suspected, discontinue JANUMET XR and institute general supportive measures in a hospital setting. Prompt hemodialysis is recommended. (5.1)

1 INDICATIONS AND USAGE

JANUMET XR is a combination of sitagliptin, a dipeptidyl peptidase-4 (DPP-4) inhibitor, and metformin hydrochloride (HCl), a biguanide indicated as an adjunct to diet and exercise to improve glycemic control in adults with type 2 diabetes mellitus. (1)

Limitations of Use:

- Not for the treatment of type 1 diabetes. (1)
- Has not been studied in patients with a history of pancreatitis. (1, 5.2)

2 DOSAGE AND ADMINISTRATION

- Take JANUMET XR orally once daily with a meal. Patients taking two JANUMET XR tablets should take the tablets together. (2.1)
- Individualize the dosage of JANUMET XR on the basis of the patient’s current regimen, effectiveness, and tolerability. (2.1)
- The maximum recommended daily dose is 100 mg of sitagliptin and 2000 mg of metformin HCl extended-release. (2.1)
- The recommended starting dose in patients not currently treated with metformin is 100 mg sitagliptin and 1000 mg metformin HCl once daily, with gradual dose escalation recommended to reduce the gastrointestinal effects due to metformin. (2.1)
- The starting dose in patients already treated with metformin should provide sitagliptin dosed as 100 mg and the dose of metformin already being taken once daily. For patients taking metformin HCl 850 mg twice daily or 1000 mg twice daily, the recommended starting dose of JANUMET XR is two 50 mg sitagliptin and 1000 mg metformin HCl extended-release tablets once daily. (2.1)
- Maintain the same total daily dose of sitagliptin and metformin when changing between JANUMET and JANUMET XR. (2.1)
- Prior to initiation, assess renal function with estimated glomerular filtration rate (eGFR) (2.2)
  - Do not use in patients with eGFR below 30 mL/min/1.73 m^2.
  - Discontinue if eGFR later falls below 30 mL/min/1.73 m^2.
  - Initiation is not recommended in patients with eGFR between 30 – 45 mL/min/1.73 m^2.
  - Assess risk/benefit of continuing if eGFR falls below 45 mL/min/1.73 m^2.
  - Limit dose of sitagliptin to 50 mg once daily if eGFR falls below 45 mL/min/1.73 m^2.
- JANUMET XR may need to be discontinued at time of, or prior to, iodinated contrast imaging procedures. (2.3)

3 DOSAGE FORMS AND STRENGTHS

JANUMET XR Tablets:

- sitagliptin 100 mg and metformin HCl 1000 mg extended-release
- sitagliptin 50 mg and metformin HCl 500 mg extended-release
- sitagliptin 50 mg and metformin HCl 1000 mg extended-release (3)

4 CONTRAINDICATIONS

- Severe renal impairment: eGFR below 30 mL/min/1.73 m^2. (4)
- Metabolic acidosis, including diabetic ketoacidosis. (4)
- History of a serious hypersensitivity reaction (e.g., anaphylaxis or angioedema) to JANUMET XR, sitagliptin, or metformin. (5.7, 6.2)

5 WARNINGS AND PRECAUTIONS

- Lactic Acidosis: See boxed warning. (5.1)
- Pancreatitis: There have been postmarketing reports of acute pancreatitis, including fatal and non-fatal hemorrhagic or necrotizing pancreatitis in patients treated with sitagliptin. If pancreatitis is suspected, promptly discontinue JANUMET XR. (5.2)
- Heart Failure: Has been observed with two other members of the DPP-4 inhibitor class. Consider risks and benefits of JANUMET XR in patients who have known risk factors for heart failure. Monitor patients for signs and symptoms. (5.3)
- Acute Renal Failure: Has been reported postmarketing sometimes requiring dialysis. Before initiating JANUMET XR and at least annually thereafter, assess renal function. (5.4)
- Vitamin B12 Deficiency: Metformin may lower vitamin B12 levels. Measure hematologic parameters annually and vitamin B12 at 2 to 3 year intervals and manage any abnormalities. (5.5)
- Hypoglycemia with Concomitant Use with Insulin or Insulin Secretagogues: Increased risk of hypoglycemia when used in combination with insulin and/or an insulin secretagogue. A lower dose of insulin or insulin secretagogue may be required. (5.6)
- Hypersensitivity Reactions: There have been postmarketing reports of serious allergic and hypersensitivity reactions in patients treated with sitagliptin, such as anaphylaxis, angioedema, and exfoliative skin conditions including Stevens-Johnson syndrome. Promptly stop JANUMET XR, assess for other potential causes, institute appropriate monitoring and treatment. (5.7)
- Severe and Disabling Arthralgia: Has been reported in patients taking DPP-4 inhibitors. Consider as a possible cause for severe joint pain and discontinue drug if appropriate. (5.8)
- Bullous Pemphigoid: There have been postmarketing reports requiring hospitalization in patients taking DPP-4 inhibitors. Tell patients to report development of blisters or erosions. If bullous pemphigoid is suspected, discontinue JANUMET XR. (5.9)

6 ADVERSE REACTIONS

- The most common adverse reactions reported in ≥5% of patients simultaneously started on sitagliptin and metformin and more commonly than in patients treated with placebo were diarrhea, upper respiratory tract infection, and headache. (6.1)

To report SUSPECTED ADVERSE REACTIONS, contact Merck Sharp & Dohme LLC at 1-877-888-4231 or FDA at 1-800-FDA-1088 or www.fda.gov/medwatch.

7 DRUG INTERACTIONS

- Carbonic anhydrase inhibitors may increase risk of lactic acidosis. Consider more frequent monitoring. (7)
- Drugs that reduce metformin clearance (such as ranolazine, vandetanib, dolutegravir, and cimetidine) may increase the accumulation of metformin. Consider the benefits and risks of concomitant use. (7)
- Alcohol can potentiate the effect of metformin on lactate metabolism. Warn patients against excessive alcohol intake. (7)

8 USE IN SPECIFIC POPULATIONS

- Females and Males of Reproductive Potential: Advise premenopausal females of the potential for an unintended pregnancy. (8.3)
- Geriatric Use: Assess renal function more frequently. (8.5)
- Hepatic Impairment: Avoid use in patients with hepatic impairment. (8.7)

FULL PRESCRIBING INFORMATION

WARNING: LACTIC ACIDOSIS

Postmarketing cases of metformin-associated lactic acidosis have resulted in death, hypothermia, hypotension, and resistant bradyarrhythmias. The onset of metformin-associated lactic acidosis is often subtle, accompanied only by nonspecific symptoms such as malaise, myalgias, respiratory distress, somnolence, and abdominal pain. Metformin-associated lactic acidosis was characterized by elevated blood lactate levels (>5 mmol/Liter), anion gap acidosis (without evidence of ketonuria or ketonemia), an increased lactate/pyruvate ratio, and metformin plasma levels generally >5 mcg/mL [see Warnings and Precautions (5.1)].

Risk factors for metformin-associated lactic acidosis include renal impairment, concomitant use of certain drugs (e.g., carbonic anhydrase inhibitors such as topiramate), age 65 years old or greater, having a radiological study with contrast, surgery and other procedures, hypoxic states (e.g., acute congestive heart failure), excessive alcohol intake, and hepatic impairment.

Steps to reduce the risk of and manage metformin-associated lactic acidosis in these high risk groups are provided in the full prescribing information [see Dosage and Administration (2.2), Contraindications (4), Warnings and Precautions (5.1), Drug Interactions (7), and Use in Specific Populations (8.6, 8.7)].

If metformin-associated lactic acidosis is suspected, immediately discontinue JANUMET XR and institute general supportive measures in a hospital setting. Prompt hemodialysis is recommended [see Warnings and Precautions (5.1)].

1 INDICATIONS AND USAGE

JANUMET® XR is indicated as an adjunct to diet and exercise to improve glycemic control in adults with type 2 diabetes mellitus.

Limitations of Use

JANUMET XR should not be used in patients with type 1 diabetes mellitus.
JANUMET XR has not been studied in patients with a history of pancreatitis. It is unknown whether patients with a history of pancreatitis are at increased risk for the development of pancreatitis while using JANUMET XR. [See Warnings and Precautions (5.2).]

2 DOSAGE AND ADMINISTRATION

2.1 Recommended Dosing

- Take JANUMET XR orally once daily with a meal. Patients taking two JANUMET XR tablets should take the two tablets together once daily.
- Individualize the dosage of JANUMET XR on the basis of the patient’s current regimen, effectiveness, and tolerability.
- The maximum recommended daily dose is 100 mg of sitagliptin and 2000 mg of metformin hydrochloride (HCl) extended-release.
- The recommended starting dose in patients not currently treated with metformin is 100 mg sitagliptin and 1000 mg metformin HCl extended-release once daily, with gradual dose escalation recommended to reduce gastrointestinal side effects associated with metformin.
- The starting dose in patients already treated with metformin should provide 100 mg sitagliptin and the previously prescribed dose of metformin.
- For patients taking metformin HCl immediate-release 850 mg twice daily or 1000 mg twice daily, the recommended starting dose of JANUMET XR is two 50 mg sitagliptin and 1000 mg metformin HCl extended-release tablets taken together once daily.
- Maintain the same total daily dose of sitagliptin and metformin when changing between JANUMET (sitagliptin and metformin HCl immediate-release) and JANUMET XR.
- Do not split, crush or chew JANUMET XR tablets.

2.2 Recommendations for Use in Renal Impairment

- Assess renal function prior to initiation of JANUMET XR and periodically thereafter.
- JANUMET XR is contraindicated in patients with an estimated glomerular filtration rate (eGFR) below 30 mL/min/1.73 m^2. Discontinue JANUMET XR if the patient's eGFR later falls below 30 mL/min/1.73 m^2 [see Contraindications (4) and Warnings and Precautions (5.1)].
- Initiation of JANUMET XR in patients with an eGFR between 30 and 45 mL/min/1.73 m^2 is not recommended.
- In patients taking JANUMET XR whose eGFR later falls below 45 mL/min/1.73 m^2, assess the benefit risk of continuing therapy and limit dose of the sitagliptin component to 50 mg once daily.

2.3 Discontinuation for Iodinated Contrast Imaging Procedures

Discontinue JANUMET XR at the time of, or prior to, an iodinated contrast imaging procedure in patients with an eGFR between 30 and 60 mL/min/1.73 m^2; in patients with a history of liver disease, alcoholism, or heart failure; or in patients who will be administered intra-arterial iodinated contrast. Re-evaluate eGFR 48 hours after the imaging procedure; restart JANUMET XR if renal function is stable [see Warnings and Precautions (5.1)].

3 DOSAGE FORMS AND STRENGTHS

Tablets:

- sitagliptin 100 mg and metformin HCl 1000 mg extended-release tablets are blue, bi-convex oval, film-coated tablets with “81” debossed on one side.
- sitagliptin 50 mg and metformin HCl 500 mg extended-release tablets are light blue, bi-convex oval, film-coated tablets with “78” debossed on one side.
- sitagliptin 50 mg and metformin HCl 1000 mg extended-release tablets are light green, bi-convex oval, film-coated tablets with “80” debossed on one side.

4 CONTRAINDICATIONS

JANUMET XR is contraindicated in patients with:

- Severe renal impairment (eGFR below 30 mL/min/1.73 m^2) [see Warnings and Precautions (5.1)].
- Acute or chronic metabolic acidosis, including diabetic ketoacidosis.
- History of a serious hypersensitivity reaction to JANUMET XR, sitagliptin, or metformin such as anaphylaxis or angioedema. [See Warnings and Precautions (5.7); Adverse Reactions (6.2).]

5 WARNINGS AND PRECAUTIONS

5.1 Lactic Acidosis

There have been postmarketing cases of metformin-associated lactic acidosis, including fatal cases. These cases had a subtle onset and were accompanied by nonspecific symptoms such as malaise, myalgias, abdominal pain, respiratory distress, or increased somnolence; however, hypothermia, hypotension and resistant bradyarrhythmias have occurred with severe acidosis. Metformin-associated lactic acidosis was characterized by elevated blood lactate concentrations (>5 mmol/Liter), anion gap acidosis (without evidence of ketonuria or ketonemia), and an increased lactate/pyruvate ratio; metformin plasma levels were generally >5 mcg/mL. Metformin decreases liver uptake of lactate increasing lactate blood levels which may increase the risk of lactic acidosis, especially in patients at risk.

If metformin-associated lactic acidosis is suspected, general supportive measures should be instituted promptly in a hospital setting, along with immediate discontinuation of JANUMET XR. In JANUMET XR-treated patients with a diagnosis or strong suspicion of lactic acidosis, prompt hemodialysis is recommended to correct the acidosis and remove accumulated metformin (metformin is dialyzable, with a clearance of up to 170 mL/min under good hemodynamic conditions). Hemodialysis has often resulted in reversal of symptoms and recovery.

Educate patients and their families about the symptoms of lactic acidosis, and if these symptoms occur instruct them to discontinue JANUMET XR and report these symptoms to their health care provider.

For each of the known and possible risk factors for metformin-associated lactic acidosis, recommendations to reduce the risk of and manage metformin-associated lactic acidosis are provided below:

Renal Impairment: The postmarketing metformin-associated lactic acidosis cases primarily occurred in patients with significant renal impairment. The risk of metformin accumulation and metformin-associated lactic acidosis increases with the severity of renal impairment because metformin is substantially excreted by the kidney. Clinical recommendations based upon the patient's renal function include [see Dosage and Administration (2.2), Clinical Pharmacology (12.3)]:

- Before initiating JANUMET XR, obtain an estimated glomerular filtration rate (eGFR).
- JANUMET XR is contraindicated in patients with an eGFR less than 30 mL/min/1.73 m^2. Discontinue JANUMET XR if the patient's eGFR later falls below 30 mL/min/1.73 m^2 [see Contraindications (4)].
- Initiation of JANUMET XR is not recommended in patients with eGFR between 30 and 45 mL/min/1.73 m^2.
- In patients taking JANUMET XR whose eGFR later falls below 45 mL/min/1.73 m^2, assess the benefit and risk of continuing therapy.
- Obtain an eGFR at least annually in all patients taking JANUMET XR. In patients at increased risk for the development of renal impairment (e.g., the elderly), renal function should be assessed more frequently.

Drug Interactions

The concomitant use of JANUMET XR with specific drugs may increase the risk of metformin-associated lactic acidosis: those that impair renal function, result in significant hemodynamic change, interfere with acid-base balance or increase metformin accumulation [see Drug Interactions (7)]. Therefore, consider more frequent monitoring of patients.

Age 65 or Greater

The risk of metformin-associated lactic acidosis increases with the patient's age because elderly patients have a greater likelihood of having hepatic, renal, or cardiac impairment than younger patients. Assess renal function more frequently in elderly patients [see Use in Specific Populations (8.5)].

Radiological Studies with Contrast

Administration of intravascular iodinated contrast agents in metformin-treated patients has led to an acute decrease in renal function and the occurrence of lactic acidosis. Stop JANUMET XR at the time of, or prior to, an iodinated contrast imaging procedure in patients with an eGFR between 30 and 60 mL/min/1.73 m^2; in patients with a history of hepatic impairment, alcoholism, or heart failure; or in patients who will be administered intra-arterial iodinated contrast. Re-evaluate eGFR 48 hours after the imaging procedure, and restart JANUMET XR if renal function is stable.

Surgery and Other Procedures

Withholding of food and fluids during surgical or other procedures may increase the risk for volume depletion, hypotension and renal impairment. JANUMET XR should be temporarily discontinued while patients have restricted food and fluid intake.

Hypoxic States

Several of the postmarketing cases of metformin-associated lactic acidosis occurred in the setting of acute congestive heart failure (particularly when accompanied by hypoperfusion and hypoxemia). Cardiovascular collapse (shock), acute myocardial infarction, sepsis, and other conditions associated with hypoxemia have been associated with lactic acidosis and may also cause prerenal azotemia. When such events occur, discontinue JANUMET XR.

Excessive Alcohol Intake

Alcohol potentiates the effect of metformin on lactate metabolism and this may increase the risk of metformin-associated lactic acidosis. Warn patients against excessive alcohol intake while receiving JANUMET XR.

Hepatic Impairment

Patients with hepatic impairment have developed with cases of metformin-associated lactic acidosis. This may be due to impaired lactate clearance resulting in higher lactate blood levels. Therefore, avoid use of JANUMET XR in patients with clinical or laboratory evidence of hepatic disease.

5.2 Pancreatitis

There have been postmarketing reports of acute pancreatitis, including fatal and non-fatal hemorrhagic or necrotizing pancreatitis, in patients taking sitagliptin with or without metformin. After initiation of JANUMET XR, patients should be observed carefully for signs and symptoms of pancreatitis. If pancreatitis is suspected, JANUMET XR should promptly be discontinued and appropriate management should be initiated. It is unknown whether patients with a history of pancreatitis are at increased risk for the development of pancreatitis while using JANUMET XR.

5.3 Heart Failure

An association between dipeptidyl peptidase-4 (DPP-4) inhibitor treatment and heart failure has been observed in cardiovascular outcomes trials for two other members of the DPP-4 inhibitor class. These trials evaluated patients with type 2 diabetes mellitus and atherosclerotic cardiovascular disease.

Consider the risks and benefits of JANUMET XR prior to initiating treatment in patients at risk for heart failure, such as those with a prior history of heart failure and a history of renal impairment, and observe these patients for signs and symptoms of heart failure during therapy. Advise patients of the characteristic symptoms of heart failure and to immediately report such symptoms. If heart failure develops, evaluate and manage according to current standards of care and consider discontinuation of JANUMET XR.

5.4 Acute Renal Failure

There have been postmarketing reports of worsening renal function in patients taking sitagliptin with or without metformin, including acute renal failure, sometimes requiring dialysis. Before initiation of therapy with JANUMET XR and at least annually thereafter, renal function should be assessed. In patients in whom development of renal dysfunction is anticipated, particularly in elderly patients, renal function should be assessed more frequently and JANUMET XR discontinued if evidence of renal impairment is present. JANUMET XR is contraindicated in patients with severe renal impairment [see Contraindications (4) and Warnings and Precautions (5.1)].

5.5 Vitamin B12 Deficiency

In controlled clinical trials of metformin of 29 weeks duration, a decrease to subnormal levels of previously normal serum vitamin B12 levels was observed in approximately 7% of patients. Such decrease, possibly due to interference with B12 absorption from the B12-intrinsic factor complex, may be associated with anemia but appears to be rapidly reversible with discontinuation of metformin or vitamin B12 supplementation. Certain individuals (those with inadequate vitamin B12 or calcium intake or absorption) appear to be predisposed to developing subnormal vitamin B12 levels. Measure hematologic parameters on an annual basis and vitamin B12 measurements at 2- to 3-year intervals in patients on JANUMET XR and manage any abnormalities [see Adverse Reactions (6.1)].

5.6 Hypoglycemia with Concomitant Use with Insulin or Insulin Secretagogues

JANUMET XR may increase the risk of hypoglycemia when combined with insulin and/or an insulin secretagogue (e.g., sulfonylurea) [see Adverse Reactions (6)]. A lower dose of insulin or insulin secretagogue may be required to minimize the risk of hypoglycemia when used in combination with JANUMET XR [see Drug Interactions (7)].

5.7 Hypersensitivity Reactions

There have been postmarketing reports of serious hypersensitivity reactions in patients treated with sitagliptin, one of the components of JANUMET XR. These reactions include anaphylaxis, angioedema, and exfoliative skin conditions including Stevens-Johnson syndrome. Onset of these reactions occurred within the first 3 months after initiation of treatment with sitagliptin, with some reports occurring after the first dose. If a hypersensitivity reaction is suspected, discontinue JANUMET XR, assess for other potential causes for the event, and institute alternative treatment for diabetes. [See Adverse Reactions (6.2).]

Use caution in a patient with a history of angioedema to another DPP-4 inhibitor because it is unknown whether such patients will be predisposed to angioedema with JANUMET XR.

5.8 Severe and Disabling Arthralgia

There have been postmarketing reports of severe and disabling arthralgia in patients taking DPP-4 inhibitors. The time to onset of symptoms following initiation of drug therapy varied from one day to years. Patients experienced relief of symptoms upon discontinuation of the medication. A subset of patients experienced a recurrence of symptoms when restarting the same drug or a different DPP-4 inhibitor. Consider DPP-4 inhibitors as a possible cause for severe joint pain and discontinue drug if appropriate.

5.9 Bullous Pemphigoid

Postmarketing cases of bullous pemphigoid requiring hospitalization have been reported with DPP-4 inhibitor use. In reported cases, patients typically recovered with topical or systemic immunosuppressive treatment and discontinuation of the DPP-4 inhibitor. Tell patients to report development of blisters or erosions while receiving JANUMET XR. If bullous pemphigoid is suspected, JANUMET XR should be discontinued and referral to a dermatologist should be considered for diagnosis and appropriate treatment.

6 ADVERSE REACTIONS

The following adverse reactions are also discussed elsewhere in the labeling:

- Lactic Acidosis [see Warnings and Precautions (5.1)]
- Pancreatitis [see Warnings and Precautions (5.2)]
- Heart Failure [see Warnings and Precautions (5.3)]
- Acute Renal Failure [see Warnings and Precautions (5.4)]
- Vitamin B12 Deficiency [see Warnings and Precautions (5.5)]
- Hypoglycemia with Concomitant Use with Insulin or Insulin Secretagogues [see Warnings and Precautions (5.6)]
- Hypersensitivity Reactions [see Warnings and Precautions (5.7)]
- Severe and Disabling Arthralgia [see Warnings and Precautions (5.8)]
- Bullous Pemphigoid [see Warnings and Precautions (5.9)]

6.1 Clinical Trials Experience

Because clinical trials are conducted under widely varying conditions, adverse reaction rates observed in the clinical trials of a drug cannot be directly compared to rates in the clinical trials of another drug and may not reflect the rates observed in practice.

Sitagliptin and Metformin Immediate-Release Coadministration in Patients with Type 2 Diabetes Inadequately Controlled on Diet and Exercise

Table 1 summarizes the most common (≥5% of patients) adverse reactions reported (regardless of investigator assessment of causality) in a 24-week placebo-controlled factorial study in which sitagliptin and metformin immediate-release were coadministered to patients with type 2 diabetes inadequately controlled on diet and exercise.

Table 1: Sitagliptin and Metformin Immediate-Release Coadministered to Patients with Type 2 Diabetes Inadequately Controlled on Diet and Exercise: Adverse Reactions Reported (Regardless of Investigator Assessment of Causality) in ≥5% of Patients Receiving Combination Therapy (and Greater than in Patients Receiving Placebo) [Intent-to-treat population.]
 | Number of Patients (%)
 | Placebo | Sitagliptin 100 mg once daily | Metformin HCl Immediate-Release 500 mg or 1000 mg twice daily [Data pooled for the patients given the lower and higher doses of metformin.] | Sitagliptin 50 mg twice daily + Metformin HCl Immediate- Release 500 mg or 1000 mg twice daily
 | N = 176 | N = 179 | N = 364 | N = 372
Diarrhea | 7 (4.0) | 5 (2.8) | 28 (7.7) | 28 (7.5)
Upper Respiratory Tract Infection | 9 (5.1) | 8 (4.5) | 19 (5.2) | 23 (6.2)
Headache | 5 (2.8) | 2 (1.1) | 14 (3.8) | 22 (5.9)

Sitagliptin Add-on Therapy in Patients with Type 2 Diabetes Inadequately Controlled on Metformin Immediate-Release Alone

In a 24-week placebo-controlled trial of sitagliptin 100 mg administered once daily added to a twice daily metformin immediate-release regimen, there were no adverse reactions reported regardless of investigator assessment of causality in ≥5% of patients and more commonly than in patients given placebo. Discontinuation of therapy due to clinical adverse reactions was similar to the placebo treatment group (sitagliptin and metformin immediate-release, 1.9%; placebo and metformin immediate-release, 2.5%).

Gastrointestinal Adverse Reactions

The incidences of pre-selected gastrointestinal adverse experiences in patients treated with sitagliptin and metformin immediate-release were similar to those reported for patients treated with metformin immediate-release alone. See Table 2.

Table 2: Pre-selected Gastrointestinal Adverse Reactions (Regardless of Investigator Assessment of Causality) Reported in Patients with Type 2 Diabetes Receiving Sitagliptin and Metformin Immediate-Release
 | Number of Patients (%)
 | Study of Sitagliptin and Metformin Immediate-Release in Patients Inadequately Controlled on Diet and Exercise |  |  |  | Study of Sitagliptin Add-on in Patients Inadequately Controlled on Metformin Immediate-Release Alone
 | Placebo | Sitagliptin 100 mg once daily | Metformin HCl Immediate-Release 500 mg or 1000 mg twice daily [Data pooled for the patients given the lower and higher doses of metformin.] | Sitagliptin 50 mg bid + Metformin HCl Immediate- Release 500 mg or 1000 mg twice daily | Placebo and Metformin HCL Immediate- Release ≥1500 mg daily | Sitagliptin 100 mg once daily and Metformin HCl Immediate- Release ≥1500 mg daily
 | N = 176 | N = 179 | N = 364 | N = 372 | N = 237 | N = 464
Diarrhea | 7 (4.0) | 5 (2.8) | 28 (7.7) | 28 (7.5) | 6 (2.5) | 11 (2.4)
Nausea | 2 (1.1) | 2 (1.1) | 20 (5.5) | 18 (4.8) | 2 (0.8) | 6 (1.3)
Vomiting | 1 (0.6) | 0 (0.0) | 2 (0.5) | 8 (2.2) | 2 (0.8) | 5 (1.1)
Abdominal Pain [Abdominal discomfort was included in the analysis of abdominal pain in the study of initial therapy.] | 4 (2.3) | 6 (3.4) | 14 (3.8) | 11 (3.0) | 9 (3.8) | 10 (2.2)

Sitagliptin in Combination with Metformin Immediate-Release and Glimepiride

In a 24-week placebo-controlled study of sitagliptin 100 mg as add-on therapy in patients with type 2 diabetes inadequately controlled on metformin immediate-release and glimepiride (sitagliptin, N=116; placebo, N=113), the adverse reactions reported regardless of investigator assessment of causality in ≥5% of patients treated with sitagliptin and more commonly than in patients treated with placebo were: hypoglycemia (Table 3) and headache (6.9%, 2.7%).

Sitagliptin in Combination with Metformin Immediate-Release and Rosiglitazone

In a placebo-controlled study of sitagliptin 100 mg as add-on therapy in patients with type 2 diabetes inadequately controlled on metformin immediate-release and rosiglitazone (sitagliptin, N=181; placebo, N=97), the adverse reactions reported regardless of investigator assessment of causality through Week 18 in ≥5% of patients treated with sitagliptin and more commonly than in patients treated with placebo were: upper respiratory tract infection (sitagliptin, 5.5%; placebo, 5.2%) and nasopharyngitis (6.1%, 4.1%). Through Week 54, the adverse reactions reported regardless of investigator assessment of causality in ≥5% of patients treated with sitagliptin and more commonly than in patients treated with placebo were: upper respiratory tract infection (sitagliptin, 15.5%; placebo, 6.2%), nasopharyngitis (11.0%, 9.3%), peripheral edema (8.3%, 5.2%), and headache (5.5%, 4.1%).

Sitagliptin in Combination with Metformin Immediate-Release and Insulin

In a 24-week placebo-controlled study of sitagliptin 100 mg as add-on therapy in patients with type 2 diabetes inadequately controlled on metformin immediate-release and insulin (sitagliptin, N=229; placebo, N=233), the only adverse reaction reported regardless of investigator assessment of causality in ≥5% of patients treated with sitagliptin and more commonly than in patients treated with placebo was hypoglycemia (Table 3).

Hypoglycemia

In the above studies (N=5), adverse reactions of hypoglycemia were based on all reports of symptomatic hypoglycemia; a concurrent glucose measurement was not required although most (77%) reports of hypoglycemia were accompanied by a blood glucose measurement ≤70 mg/dL. When the combination of sitagliptin and metformin immediate-release was coadministered with a sulfonylurea or with insulin, the percentage of patients reporting at least one adverse reaction of hypoglycemia was higher than that observed with placebo and metformin immediate-release coadministered with a sulfonylurea or with insulin (Table 3).

Table 3: Incidence and Rate of Hypoglycemia [Adverse reactions of hypoglycemia were based on all reports of symptomatic hypoglycemia; a concurrent glucose measurement was not required: Intent-to-treat population.] (Regardless of Investigator Assessment of Causality) in Placebo-Controlled Clinical Studies of Sitagliptin in Combination with Metformin Immediate-Release Coadministered with Glimepiride or Insulin
Add-On to Glimepiride + Metformin Immediate-Release (24 weeks) | Sitagliptin 100 mg + Metformin Immediate-Release + Glimepiride | Placebo + Metformin Immediate-Release + Glimepiride
 | N = 116 | N = 113
Overall (%) | 19 (16.4) | 1 (0.9)
Rate (episodes/patient-year) [Based on total number of events (i.e., a single patient may have had multiple events).] | 0.82 | 0.02
Severe (%) [Severe events of hypoglycemia were defined as those events requiring medical assistance or exhibiting depressed level/loss of consciousness or seizure.] | 0 (0.0) | 0 (0.0)
Add-On to Insulin + Metformin Immediate-Release (24 weeks) | Sitagliptin 100 mg + Metformin Immediate-Release + Insulin | Placebo + Metformin Immediate-Release + Insulin
 | N = 229 | N = 233
Overall (%) | 35 (15.3) | 19 (8.2)
Rate (episodes/patient-year) | 0.98 | 0.61
Severe (%) | 1 (0.4) | 1 (0.4)

The overall incidence of reported adverse reactions of hypoglycemia in patients with type 2 diabetes inadequately controlled on diet and exercise was 0.6% in patients given placebo, 0.6% in patients given sitagliptin alone, 0.8% in patients given metformin immediate-release alone, and 1.6% in patients given sitagliptin in combination with metformin immediate-release. In patients with type 2 diabetes inadequately controlled on metformin immediate-release alone, the overall incidence of adverse reactions of hypoglycemia was 1.3% in patients given add-on sitagliptin and 2.1% in patients given add-on placebo.

In the study of sitagliptin and add-on combination therapy with metformin immediate-release and rosiglitazone, the overall incidence of hypoglycemia was 2.2% in patients given add-on sitagliptin and 0.0% in patients given add-on placebo through Week 18. Through Week 54, the overall incidence of hypoglycemia was 3.9% in patients given add-on sitagliptin and 1.0% in patients given add-on placebo.

In an additional 30-week placebo-controlled study of patients with type 2 diabetes inadequately controlled with metformin comparing the maintenance of sitagliptin 100 mg versus withdrawal of sitagliptin when initiating basal insulin therapy, the event rate and incidence of documented symptomatic hypoglycemia (blood glucose measurement ≤70 mg/dL) did not differ between the sitagliptin and placebo groups.

Vital Signs and Electrocardiograms

With the combination of sitagliptin and metformin immediate-release, no clinically meaningful changes in vital signs or in electrocardiogram parameters (including the QTc interval) were observed.

Pancreatitis

In a pooled analysis of 19 double-blind clinical trials that included data from 10,246 patients randomized to receive sitagliptin 100 mg/day (N=5429) or corresponding (active or placebo) control (N=4817), the incidence of acute pancreatitis was 0.1 per 100 patient-years in each group (4 patients with an event in 4708 patient-years for sitagliptin and 4 patients with an event in 3942 patient-years for control).

Sitagliptin

The most common adverse experience in sitagliptin monotherapy reported regardless of investigator assessment of causality in ≥5% of patients and more commonly than in patients given placebo was nasopharyngitis.

Metformin Extended-Release

In a 24-week clinical trial in which extended-release metformin or placebo was added to glyburide therapy, the most common (>5% and greater than placebo) adverse reactions in the combined treatment group were hypoglycemia (13.7% vs. 4.9%), diarrhea (12.5% vs. 5.6%), and nausea (6.7% vs. 4.2%).

Laboratory Tests

Sitagliptin

The incidence of laboratory adverse reactions was similar in patients treated with sitagliptin and metformin immediate-release (7.6%) compared to patients treated with placebo and metformin (8.7%). In most but not all studies, a small increase in white blood cell count (approximately 200 cells/microL difference in WBC vs. placebo; mean baseline WBC approximately 6600 cells/microL) was observed due to a small increase in neutrophils. This change in laboratory parameters is not considered to be clinically relevant.

Metformin

In controlled clinical trials of metformin of 29 weeks duration, a decrease to subnormal levels of previously normal serum vitamin B12 levels, without clinical manifestations, was observed in approximately 7% of patients. Such decrease, possibly due to interference with B12 absorption from the B12-intrinsic factor complex, is, however, very rarely associated with anemia and appears to be rapidly reversible with discontinuation of metformin or vitamin B12 supplementation.

6.2 Postmarketing Experience

Additional adverse reactions have been identified during postapproval use of sitagliptin with metformin, sitagliptin, or metformin. Because these reactions are reported voluntarily from a population of uncertain size, it is generally not possible to reliably estimate their frequency or establish a causal relationship to drug exposure.

Hypersensitivity reactions including anaphylaxis, angioedema, rash, urticaria, cutaneous vasculitis, and exfoliative skin conditions including Stevens-Johnson syndrome; upper respiratory tract infection; hepatic enzyme elevations; acute pancreatitis, including fatal and non-fatal hemorrhagic and necrotizing pancreatitis [see Indications and Usage (1)]; worsening renal function, including acute renal failure (sometimes requiring dialysis) and tubulointerstitial nephritis; severe and disabling arthralgia; bullous pemphigoid; constipation; vomiting; headache; myalgia; pain in extremity; back pain; pruritus; mouth ulceration; stomatitis; cholestatic, hepatocellular, and mixed hepatocellular liver injury; rhabdomyolysis.

7 DRUG INTERACTIONS

Table 4 presents clinically significant drug interactions with JANUMET XR:

Table 4: Clinically Significant Drug Interactions with JANUMET XR
Carbonic Anhydrase Inhibitors
Clinical Impact: | Carbonic anhydrase inhibitors frequently cause a decrease in serum bicarbonate and induce non-anion gap, hyperchloremic metabolic acidosis. Concomitant use of these drugs with JANUMET XR may increase the risk for lactic acidosis.
Intervention: | Consider more frequent monitoring of these patients.
Examples: | Topiramate, zonisamide, acetazolamide or dichlorphenamide.
Drugs that Reduce Metformin Clearance
Clinical Impact: | Concomitant use of drugs that interfere with common renal tubular transport systems involved in the renal elimination of metformin (e.g., organic cationic transporter-2 [OCT2] / multidrug and toxin extrusion [MATE] inhibitors) could increase systemic exposure to metformin and may increase the risk for lactic acidosis [see Clinical Pharmacology (12.3)].
Intervention: | Consider the benefits and risks of concomitant use with JANUMET XR.
Examples: | Ranolazine, vandetanib, dolutegravir, and cimetidine.
Alcohol
Clinical Impact: | Alcohol is known to potentiate the effect of metformin on lactate metabolism.
Intervention: | Warn patients against alcohol intake while receiving JANUMET XR.
Insulin Secretagogues or Insulin
Clinical Impact: | Coadministration of JANUMET XR with an insulin secretagogue (e.g., sulfonylurea) or insulin may increase the risk of hypoglycemia.
Intervention: | Patients receiving an insulin secretagogue or insulin may require lower doses of the insulin secretagogue or insulin.
Drugs Affecting Glycemic Control
Clinical Impact: | Certain drugs tend to produce hyperglycemia and may lead to loss of glycemic control.
Intervention: | When such drugs are administered to a patient receiving JANUMET XR, observe the patient closely for loss of blood glucose control. When such drugs are withdrawn from a patient receiving JANUMET XR, observe the patient closely for hypoglycemia.
Examples: | Thiazides and other diuretics, corticosteroids, phenothiazines, thyroid products, estrogens, oral contraceptives, phenytoin, nicotinic acid, sympathomimetics, calcium channel blockers, and isoniazid.

8 USE IN SPECIFIC POPULATIONS

8.1 Pregnancy

Risk Summary

The limited available data with JANUMET XR in pregnant women are not sufficient to inform a drug-associated risk for major birth defects and miscarriage. Published studies with metformin use during pregnancy have not reported a clear association with metformin and major birth defect or miscarriage risk [see Data]. There are risks to the mother and fetus associated with poorly controlled diabetes in pregnancy [see Clinical Considerations]. No adverse developmental effects were observed when sitagliptin was administered to pregnant rats and rabbits during organogenesis at oral doses up to 30-times and 20-times, respectively, the 100 mg clinical dose, based on AUC. No adverse developmental effects were observed when metformin was administered to pregnant Sprague Dawley rats and rabbits during organogenesis at doses up to 2- and 6-times, respectively, a 2000 mg clinical dose, based on body surface area [see Data].

The estimated background risk of major birth defects is 6-10% in women with pre-gestational diabetes with a Hemoglobin A1c >7% and has been reported to be as high as 20-25% in women with a Hemoglobin A1c >10%. In the U.S. general population, the estimated background risk of major birth defects and miscarriage in clinically recognized pregnancies is 2-4% and 15-20%, respectively.

Clinical Considerations

Disease-Associated Maternal and/or Embryo/Fetal Risk

Poorly controlled diabetes in pregnancy increases the maternal risk for diabetic ketoacidosis, pre-eclampsia, spontaneous abortions, preterm delivery, and delivery complications. Poorly controlled diabetes increases the fetal risk for major birth defects, still birth, and macrosomia related morbidity.

Data

Human Data

Published data from post-marketing studies do not report a clear association with metformin and major birth defects, miscarriage, or adverse maternal or fetal outcomes when metformin is used during pregnancy. However, these studies cannot definitely establish the absence of any risk because of methodological limitations, including small sample size and inconsistent comparator groups.

Animal Data

Sitagliptin and Metformin

No animal reproduction studies were conducted with the coadministration of sitagliptin and metformin.

Sitagliptin

In embryo-fetal development studies, sitagliptin administered to pregnant rats and rabbits during organogenesis (gestation day 6 to 20) did not adversely affect developmental outcomes at oral doses up to 250 mg/kg (30-times the 100 mg clinical dose) and 125 mg/kg (20-times the 100 mg clinical dose), respectively, based on AUC. Higher doses in rats associated with maternal toxicity increased the incidence of rib malformations in offspring at 1000 mg/kg, or approximately 100-times the clinical dose, based on AUC. Placental transfer of sitagliptin was observed in pregnant rats and rabbits.

Sitagliptin administered to female rats from gestation day 6 to lactation day 21 caused no functional or behavioral toxicity in offspring of rats at doses up to 1000 mg/kg.

Metformin

Metformin did not cause adverse developmental effects when administered to pregnant Sprague Dawley rats and rabbits up to 600 mg/kg/day during the period of organogenesis. This represents an exposure of about 2- and 6-times a 2000 mg clinical dose based on body surface area (mg/m^2) for rats and rabbits, respectively.

8.2 Lactation

Risk Summary

There is no information regarding the presence of JANUMET XR in human milk, the effects on the breastfed infant, or the effects on milk production. Limited published studies report that metformin is present in human milk [see Data]. There are no reports of adverse effects on breastfed infants exposed to metformin. There is no information on the effects of metformin on milk production. Sitagliptin is present in rat milk and therefore possibly present in human milk [see Data]. The developmental and health benefits of breastfeeding should be considered along with the mother's clinical need for JANUMET XR and any potential adverse effects on the breastfed infant from JANUMET XR or from the underlying maternal condition.

Data

Sitagliptin

Sitagliptin is secreted in the milk of lactating rats at a milk to plasma ratio of 4:1.

Metformin

Published clinical lactation studies report that metformin is present in human milk, which resulted in infant doses approximately 0.11% to 1% of the maternal weight-adjusted dosage and a milk/plasma ratio ranging between 0.13 and 1. However, the studies were not designed to definitely establish the risk of use of metformin during lactation because of small sample size and limited adverse event data collected in infants.

8.3 Females and Males of Reproductive Potential

Discuss the potential for unintended pregnancy with premenopausal women as therapy with metformin may result in ovulation in some anovulatory women.

8.4 Pediatric Use

The safety and effectiveness of JANUMET XR have not been established in pediatric patients.

Three 20-week double-blind, placebo-controlled studies each with 34-week extensions were conducted to evaluate the efficacy and safety of sitagliptin in 410 pediatric patients aged 10 to 17 years with inadequately controlled type 2 diabetes, with or without insulin therapy (HbA1c 6.5-10% for patients not on insulin, HbA1c 7-10% for patients on insulin). At study entry, patients in study 1 were not treated with oral antihyperglycemic agents; patients in studies 2 and 3 were on maximally tolerated metformin therapy. The primary efficacy endpoint was the change from baseline in HbA1c after 20 weeks of therapy. The pre-specified primary efficacy analyses included data from study 1 and pooled data from studies 2 and 3, regardless of glycemic rescue or treatment discontinuation.

In both efficacy analyses, the effect of treatment with sitagliptin was not significantly different from placebo. In study 1, the mean baseline HbA1c was 7.5%, and 12% of patients were on insulin therapy. At week 20, the change from baseline in HbA1c in patients treated with sitagliptin (N=95) was 0.06% compared to 0.23% in patients treated with placebo (N=95), a difference of -0.17% (95% CI: -0.62, 0.28). In studies 2 and 3, the mean baseline HbA1c was 8.0%, 15% of patients were on insulin and 72% were on metformin HCl doses of greater than 1,500 mg daily. At week 20, the change from baseline in HbA1c in patients treated with sitagliptin (N=107) was -0.23% compared to 0.09% in patients treated with placebo (N=113), a difference of -0.33% (95% CI: -0.70, 0.05).

8.5 Geriatric Use

JANUMET XR

In general, dose selection for an elderly patient should be cautious, usually starting at the low end of the dosing range, reflecting the greater frequency of decreased hepatic, renal, or cardiac function, and concomitant disease or other drug therapy and the higher risk of lactic acidosis. Renal function should be assessed more frequently in elderly patients. [See Contraindications (4); Warnings and Precautions (5.1, 5.4); Clinical Pharmacology (12.3).]

Sitagliptin

Of the total number of subjects (N=3884) in clinical studies of sitagliptin, 725 patients were 65 years and over, while 61 patients were 75 years and over. No overall differences in safety or effectiveness were observed between subjects 65 years and over and younger subjects. While this and other reported clinical experience have not identified differences in responses between the elderly and younger patients, greater sensitivity of some older individuals cannot be ruled out.

Metformin

Controlled clinical studies of metformin did not include sufficient numbers of elderly patients to determine whether they respond differently from younger patients, although other reported clinical experience has not identified differences in responses between the elderly and young patients.

8.6 Renal Impairment

JANUMET XR

The dose of the sitagliptin component should be limited to 50 mg once daily if eGFR falls below 45 mL/min/1.73 m^2. JANUMET XR is contraindicated in severe renal impairment, patients with an eGFR below 30 mL/min/1.73 m^2. [See Dosage and Administration (2.2), Contraindications (4), Warnings and Precautions (5.1) and Clinical Pharmacology (12.3).]

Sitagliptin

Sitagliptin is excreted by the kidney, and sitagliptin exposure is increased in patients with renal impairment. [See Clinical Pharmacology (12.3).]

Metformin

Metformin is substantially excreted by the kidney, and the risk of metformin accumulation and lactic acidosis increases with the degree of renal impairment.

8.7 Hepatic Impairment

Use of metformin in patients with hepatic impairment has been associated with some cases of lactic acidosis. JANUMET XR is not recommended in patients with hepatic impairment. [See Warnings and Precautions (5.1).]

10 OVERDOSAGE

In the event of overdose with JANUMET XR, contact the Poison Control Center.

In the event of an overdose, it is reasonable to employ supportive measures, e.g., remove unabsorbed material from the gastrointestinal tract, employ clinical monitoring (including obtaining an electrocardiogram), and institute supportive therapy as indicated by the patient's clinical status.

Sitagliptin is modestly dialyzable. In clinical studies, approximately 13.5% of the dose was removed over a 3- to 4-hour hemodialysis session. Prolonged hemodialysis may be considered if clinically appropriate. It is not known if sitagliptin is dialyzable by peritoneal dialysis.

Overdose of metformin has occurred, including ingestion of amounts greater than 50 grams. Hypoglycemia was reported in approximately 10% of cases, but no causal association with metformin has been established. Lactic acidosis has been reported in approximately 32% of metformin overdose cases [see Warnings and Precautions (5.1)]. Metformin is dialyzable with a clearance of up to 170 mL/min under good hemodynamic conditions. Therefore, hemodialysis may be useful for removal of accumulated drug from patients in whom metformin overdosage is suspected.

11 DESCRIPTION

JANUMET XR tablets for oral use contain two antihyperglycemic medications: sitagliptin and metformin extended-release.

Sitagliptin

Sitagliptin is an orally-active inhibitor of the dipeptidyl peptidase-4 (DPP-4) enzyme. Sitagliptin phosphate monohydrate drug substance is used to manufacture JANUMET XR. Sitagliptin phosphate monohydrate is described chemically as 7-[(3R)-3-amino-1-oxo-4-(2,4,5-trifluorophenyl)butyl]-5,6,7,8-tetrahydro-3-(trifluoromethyl)-1,2,4-triazolo[4,3-α]pyrazine phosphate (1:1) monohydrate with an empirical formula of C16H15F6N5O•H3PO4•H2O and a molecular weight of 523.32. The structural formula is:

Sitagliptin phosphate monohydrate is a white to off-white, crystalline, non-hygroscopic powder. It is soluble in water and N,N-dimethyl formamide; slightly soluble in methanol; very slightly soluble in ethanol, acetone, and acetonitrile; and insoluble in isopropanol and isopropyl acetate.

Metformin

Metformin HCl (N,N-dimethylimidodicarbonimidic diamide HCl) is a white to off-white crystalline compound with a molecular formula of C4H11N5•HCl and a molecular weight of 165.63. Metformin HCl is freely soluble in water and is practically insoluble in acetone, ether, and chloroform. The pKa of metformin HCl is 12.4. The pH of a 1% aqueous solution of metformin HCl is 6.68. The structural formula is as shown:

JANUMET XR

JANUMET XR is available as film-coated tablets containing:

- 64.25 mg sitagliptin monohydrate equivalent to 50 mg sitagliptin and 389.93 mg of metformin equivalent to 500 mg metformin HCl (JANUMET XR 50/500).
- 64.25 mg sitagliptin monohydrate equivalent to 50 mg sitagliptin and 779.86 mg of metformin equivalent to 1000 mg metformin HCl (JANUMET XR 50/1000).
- 128.5 mg sitagliptin monohydrate equivalent to 100 mg sitagliptin and 779.86 mg of metformin equivalent to 1000 mg metformin HCl (JANUMET XR 100/1000).

All doses of JANUMET XR contain the following inactive ingredients: povidone, hypromellose, colloidal silicon dioxide, sodium stearyl fumarate, propyl gallate, polyethylene glycol, and kaolin. The JANUMET XR 50 mg/500 mg tablet contains the additional inactive ingredient microcrystalline cellulose. In addition, the film coating for all doses contains the following inactive ingredients: hypromellose, hydroxypropyl cellulose, titanium dioxide, FD&C #2/Indigo Carmine Aluminum Lake and carnauba wax. The JANUMET XR 50 mg/1000 mg tablet film coating also contains the inactive ingredient yellow iron oxide.

12 CLINICAL PHARMACOLOGY

12.1 Mechanism of Action

JANUMET XR

JANUMET XR tablets combine two antihyperglycemic agents with complementary mechanisms of action to improve glycemic control in adults with type 2 diabetes mellitus: sitagliptin, a dipeptidyl peptidase-4 (DPP-4) inhibitor, and metformin extended-release, a member of the biguanide class.

Sitagliptin

Sitagliptin is a DPP-4 inhibitor, which exerts its actions in patients with type 2 diabetes by slowing the inactivation of incretin hormones. Concentrations of the active intact hormones are increased by sitagliptin, thereby increasing and prolonging the action of these hormones. Incretin hormones, including glucagon-like peptide-1 (GLP-1) and glucose-dependent insulinotropic polypeptide (GIP), are released by the intestine throughout the day, and levels are increased in response to a meal. These hormones are rapidly inactivated by the enzyme DPP-4. The incretins are part of an endogenous system involved in the physiologic regulation of glucose homeostasis. When blood glucose concentrations are normal or elevated, GLP-1 and GIP increase insulin synthesis and release from pancreatic beta cells by intracellular signaling pathways involving cyclic AMP. GLP-1 also lowers glucagon secretion from pancreatic alpha cells, leading to reduced hepatic glucose production. By increasing and prolonging active incretin levels, sitagliptin increases insulin release and decreases glucagon levels in the circulation in a glucose-dependent manner. Sitagliptin demonstrates selectivity for DPP-4 and does not inhibit DPP-8 or DPP-9 activity in vitro at concentrations approximating those from therapeutic doses.

Metformin

Metformin is a biguanide that improves glycemic control in patients with type 2 diabetes mellitus, lowering both basal and postprandial plasma glucose. Metformin decreases hepatic glucose production, decreases intestinal absorption of glucose, and improves insulin sensitivity by increasing peripheral glucose uptake and utilization. With metformin therapy, insulin secretion remains unchanged while fasting insulin levels and day-long plasma insulin response may decrease.

12.2 Pharmacodynamics

Sitagliptin

In patients with type 2 diabetes mellitus, administration of sitagliptin led to inhibition of DPP-4 enzyme activity for a 24-hour period. After an oral glucose load or a meal, this DPP-4 inhibition resulted in a 2- to 3-fold increase in circulating levels of active GLP-1 and GIP, decreased glucagon concentrations, and increased responsiveness of insulin release to glucose, resulting in higher C-peptide and insulin concentrations. The rise in insulin with the decrease in glucagon was associated with lower fasting glucose concentrations and reduced glucose excursion following an oral glucose load or a meal.

In studies with healthy subjects, sitagliptin did not lower blood glucose or cause hypoglycemia.

Sitagliptin and Metformin Coadministration

In a two-day study in healthy subjects, sitagliptin alone increased active GLP-1 concentrations, whereas metformin alone increased active and total GLP-1 concentrations to similar extents. Coadministration of sitagliptin and metformin had an additive effect on active GLP-1 concentrations. Sitagliptin, but not metformin, increased active GIP concentrations. It is unclear what these findings mean for changes in glycemic control in patients with type 2 diabetes mellitus.

Cardiac Electrophysiology

In a randomized, placebo-controlled crossover study, 79 healthy subjects were administered a single oral dose of sitagliptin 100 mg, sitagliptin 800 mg (8 times the recommended dose), and placebo. At the recommended dose of 100 mg, there was no effect on the QTc interval obtained at the peak plasma concentration, or at any other time during the study. Following the 800-mg dose, the maximum increase in the placebo-corrected mean change in QTc from baseline at 3 hours postdose was 8.0 msec. This increase is not considered to be clinically significant. At the 800-mg dose, peak sitagliptin plasma concentrations were approximately 11 times higher than the peak concentrations following a 100-mg dose.

In patients with type 2 diabetes mellitus administered sitagliptin 100 mg (N=81) or sitagliptin 200 mg (N=63) daily, there were no meaningful changes in QTc interval based on ECG data obtained at the time of expected peak plasma concentration.

12.3 Pharmacokinetics

JANUMET XR

After administration of two JANUMET XR 50 mg/1000 mg tablets once daily with the evening meal for 7 days in healthy adult subjects, steady-state for sitagliptin and metformin is reached by Day 4 and 5, respectively.

Sitagliptin

The pharmacokinetics of sitagliptin have been extensively characterized in healthy subjects and patients with type 2 diabetes mellitus. Following a single oral 100-mg dose to healthy volunteers, mean plasma AUC of sitagliptin was 8.52 µM•hr, Cmax was 950 nM, and apparent terminal half-life (t½) was 12.4 hours. Plasma AUC of sitagliptin increased in a dose-proportional manner and increased approximately 14% following 100 mg doses at steady-state compared to the first dose. The intra-subject and inter-subject coefficients of variation for sitagliptin AUC were small (5.8% and 15.1%). The pharmacokinetics of sitagliptin was generally similar in healthy subjects and in patients with type 2 diabetes mellitus.

Absorption

JANUMET XR

After administration of JANUMET XR tablets once daily, the median Tmax value for sitagliptin and metformin at steady state is approximately 3 and 8 hours postdose, respectively. The median Tmax value for sitagliptin and metformin after administration of a single tablet of JANUMET is 3 and 3.5 hours postdose, respectively.

Effect of Food

After administration of JANUMET XR tablets with a high-fat breakfast, the AUC for sitagliptin was not altered. The mean Cmax was decreased by 17%, although the median Tmax was unchanged relative to the fasted state. After administration of JANUMET XR with a high-fat breakfast, the AUC for metformin increased 62%, the Cmax for metformin decreased by 9%, and the median Tmax for metformin occurred 2 hours later relative to the fasted state.

Sitagliptin

After oral administration of a 100 mg dose to healthy subjects, sitagliptin was rapidly absorbed with peak plasma concentrations (median Tmax) occurring 1 to 4 hours postdose. The absolute bioavailability of sitagliptin is approximately 87%.

Effect of Food

Coadministration of a high-fat meal with sitagliptin had no effect on the pharmacokinetics of sitagliptin.

Metformin

The absolute bioavailability of a metformin HCl 500-mg tablet given under fasting conditions is approximately 50-60%. Studies using single oral doses of metformin HCl tablets 500 mg to 1,500 mg, and 850 mg to 2,550 mg (approximately 1.3 times the maximum recommended daily dosage), indicate that there is a lack of dose proportionality with increasing doses, which is due to decreased absorption rather than an alteration in elimination.

Effect of Food

Food decreases the extent of and slightly delays the absorption of metformin, as shown by approximately a 40% lower mean peak plasma concentration (Cmax), a 25% lower area under the plasma concentration versus time curve (AUC), and a 35-minute prolongation of time to peak plasma concentration (Tmax) following administration of a single 850-mg tablet of metformin HCl with food, compared to the same tablet strength administered fasting. The clinical relevance of these decreases is unknown.

Distribution

Sitagliptin

The mean volume of distribution at steady state following a single 100-mg intravenous dose of sitagliptin to healthy subjects is approximately 198 liters. The fraction of sitagliptin reversibly bound to plasma proteins is low (38%).

Metformin

Distribution studies with extended-release metformin have not been conducted; however, the apparent volume of distribution (V/F) of metformin following single oral doses of immediate-release metformin HCl tablets 850 mg averaged 654 ± 358 L. Metformin is negligibly bound to plasma proteins. Metformin partitions into erythrocytes, most likely as a function of time. At usual clinical doses and dosing schedules of metformin tablets, steady-state plasma concentrations of metformin are reached within 24-48 hours and are generally <1 mcg/mL.

Elimination

Sitagliptin

Approximately 79% of sitagliptin is excreted unchanged in the urine with metabolism being a minor pathway of elimination. The apparent terminal t1/2 following a 100 mg oral dose of sitagliptin was approximately 12.4 hours and renal clearance was approximately 350 mL/min.

Metformin

Following oral administration, approximately 90% of the absorbed drug is eliminated via the renal route within the first 24 hours, with a plasma elimination half-life of approximately 6.2 hours. In blood, the elimination half-life is approximately 17.6 hours, suggesting that the erythrocyte mass may be a compartment of distribution.

Metabolism

Sitagliptin

Following a [^14C]sitagliptin oral dose, approximately 16% of the radioactivity was excreted as metabolites of sitagliptin. Six metabolites were detected at trace levels and are not expected to contribute to the plasma DPP-4 inhibitory activity of sitagliptin. In vitro studies indicated that the primary enzyme responsible for the limited metabolism of sitagliptin was CYP3A4, with contribution from CYP2C8.

Metformin

Intravenous single-dose studies in normal subjects demonstrate that metformin is excreted unchanged in the urine and does not undergo hepatic metabolism (no metabolites have been identified in humans) or biliary excretion. Metabolism studies with extended-release metformin tablets have not been conducted.

Excretion

Sitagliptin

Following administration of an oral [^14C]sitagliptin dose to healthy subjects, approximately 100% of the administered radioactivity was eliminated in feces (13%) or urine (87%) within one week of dosing.

Elimination of sitagliptin occurs primarily via renal excretion and involves active tubular secretion. Sitagliptin is a substrate for human organic anion transporter-3 (hOAT-3), which may be involved in the renal elimination of sitagliptin. The clinical relevance of hOAT-3 in sitagliptin transport has not been established. Sitagliptin is also a substrate of p-glycoprotein (P-gp), which may also be involved in mediating the renal elimination of sitagliptin. However, cyclosporine, a P-gp inhibitor, did not reduce the renal clearance of sitagliptin.

Metformin

Elimination of metformin occurs primarily via renal excretion. Renal clearance is approximately 3.5 times greater than creatinine clearance, which indicates that tubular secretion is the major route of metformin elimination.

Specific Populations

Patients with Renal Impairment

JANUMET XR

Studies characterizing the pharmacokinetics of sitagliptin and metformin after administration of JANUMET XR in renally impaired patients have not been performed [see Dosage and Administration (2.2)].

Sitagliptin

An approximately 2-fold increase in the plasma AUC of sitagliptin was observed in patients with moderate renal impairment with eGFR of 30 to less than 45 mL/min/1.73 m^2, and an approximately 4-fold increase was observed in patients with severe renal impairment including patients with end-stage renal disease (ESRD) on hemodialysis, as compared to normal healthy control subjects. [See Dosage and Administration (2.2).]

Metformin

In patients with decreased renal function, the plasma and blood half-life of metformin is prolonged and the renal clearance is decreased [see Contraindications (4), Warnings and Precautions (5.1)].

Patients with Hepatic Impairment

JANUMET XR

Studies characterizing the pharmacokinetics of sitagliptin and metformin after administration of JANUMET XR in patients with hepatic impairment have not been performed.

Sitagliptin

In patients with moderate hepatic impairment (Child-Pugh score 7 to 9), mean AUC and Cmax of sitagliptin increased approximately 21% and 13%, respectively, compared to healthy matched controls following administration of a single 100-mg dose of sitagliptin. These differences are not considered to be clinically meaningful. There is no clinical experience in patients with severe hepatic impairment (Child-Pugh score >9) [see Use in Specific Populations (8.7)].

Metformin

No pharmacokinetic studies of metformin have been conducted in patients with hepatic impairment.

Effects of Age, Body Mass Index (BMI), Gender, and Race

Sitagliptin

Based on a population pharmacokinetic analysis or a composite analysis of available pharmacokinetic data, BMI, gender, and race do not have a clinically meaningful effect on the pharmacokinetics of sitagliptin. When the effects of age on renal function are taken into account, age alone did not have a clinically meaningful impact on the pharmacokinetics of sitagliptin based on a population pharmacokinetic analysis. Elderly subjects (65 to 80 years) had approximately 19% higher plasma concentrations of sitagliptin compared to younger subjects.

Metformin

Limited data from controlled pharmacokinetic studies of metformin in healthy elderly subjects suggest that total plasma clearance of metformin is decreased, the half-life is prolonged, and Cmax is increased, compared to healthy young subjects. From these data, it appears that the change in metformin pharmacokinetics with aging is primarily accounted for by a change in renal function.

Metformin pharmacokinetic parameters did not differ significantly between normal subjects and patients with type 2 diabetes mellitus when analyzed according to gender. Similarly, in controlled clinical studies in patients with type 2 diabetes mellitus, the antihyperglycemic effect of metformin was comparable in males and females.

No studies of metformin pharmacokinetic parameters according to race have been performed. In controlled clinical studies of metformin in patients with type 2 diabetes mellitus, the antihyperglycemic effect was comparable in Whites (n=249), Blacks (n=51), and Hispanics (n=24).

Drug Interaction Studies

JANUMET XR

Coadministration of multiple doses of sitagliptin (50 mg) and metformin HCl (1000 mg) given twice daily did not meaningfully alter the pharmacokinetics of either sitagliptin or metformin in patients with type 2 diabetes.

Pharmacokinetic drug interaction studies with JANUMET XR have not been performed; however, such studies have been conducted with the individual components of JANUMET XR (sitagliptin and metformin extended-release).

Sitagliptin

In Vitro Assessment of Drug Interactions

Sitagliptin is not an inhibitor of CYP isozymes CYP3A4, 2C8, 2C9, 2D6, 1A2, 2C19 or 2B6, and is not an inducer of CYP3A4. Sitagliptin is a P-gp substrate, but does not inhibit P-gp mediated transport of digoxin. Based on these results, sitagliptin is considered unlikely to cause interactions with other drugs that utilize these pathways.

Sitagliptin is not extensively bound to plasma proteins. Therefore, the propensity of sitagliptin to be involved in clinically meaningful drug-drug interactions mediated by plasma protein binding displacement is very low.

In Vivo Assessment of Drug Interactions

Effects of Sitagliptin on Other Drugs

In clinical studies, sitagliptin did not meaningfully alter the pharmacokinetics of metformin, glyburide, simvastatin, rosiglitazone, digoxin, warfarin, or an oral contraception (ethinyl estradiol and norethindrone) (Table 5), providing in vivo evidence of a low propensity for causing drug interactions with substrates of CYP3A4, CYP2C8, CYP2C9, P-gp, and organic cationic transporter (OCT).

Table 5: Effect of Sitagliptin on Systemic Exposure of Coadministered Drugs
Coadministered Drug | Dose of Coadministered Drug [All doses administered as single dose unless otherwise specified.] | Dose of Sitagliptin | Geometric Mean Ratio (ratio with/without sitagliptin) No Effect = 1.00
 |  |  |  | AUC [AUC is reported as AUC0-∞ unless otherwise specified.] | Cmax
Digoxin | 0.25 mg [Multiple dose.] once daily for 10 days | 100 mg once daily for 10 days | Digoxin | 1.11 [AUC0-24hr.] | 1.18
Glyburide | 1.25 mg | 200 mg once daily for 6 days | Glyburide | 1.09 | 1.01
Simvastatin | 20 mg | 200 mg once daily for 5 days | Simvastatin | 0.85 [AUC0-last.] | 0.80
Simvastatin | 20 mg | 200 mg once daily for 5 days | Simvastatin Acid | 1.12 | 1.06
Rosiglitazone | 4 mg | 200 mg once daily for 5 days | Rosiglitazone | 0.98 | 0.99
Warfarin | 30 mg single dose on day 5 | 200 mg once daily for 11 days | S(-) Warfarin | 0.95 | 0.89
Warfarin | 30 mg single dose on day 5 | 200 mg once daily for 11 days | R(+) Warfarin | 0.99 | 0.89
Ethinyl estradiol and norethindrone | 21 days once daily of 35 µg ethinyl estradiol with norethindrone 0.5 mg × 7 days, 0.75 mg × 7 days, 1.0 mg × 7 days | 200 mg once daily for 21 days | Ethinyl estradiol | 0.99 | 0.97
Ethinyl estradiol and norethindrone | 21 days once daily of 35 µg ethinyl estradiol with norethindrone 0.5 mg × 7 days, 0.75 mg × 7 days, 1.0 mg × 7 days | 200 mg once daily for 21 days | Norethindrone | 1.03 | 0.98
Metformin HCl | 1000 mg twice daily for 14 days | 50 mg twice daily for 7 days | Metformin | 1.02 [AUC0-12hr.] | 0.97

Effects of Other Drugs on Sitagliptin

Clinical data described below suggest that sitagliptin is not susceptible to clinically meaningful interactions by coadministered medications (Table 6).

Table 6: Effect of Coadministered Drugs on Systemic Exposure of Sitagliptin
Coadministered Drug | Dose of Coadministered Drug [All doses administered as single dose unless otherwise specified.] | Dose of Sitagliptin | Geometric Mean Ratio (ratio with/without coadministered drug) No Effect = 1.00
 |  |  |  | AUC [AUC is reported as AUC0-∞ unless otherwise specified.] | Cmax
Cyclosporine | 600 mg once daily | 100 mg once daily | Sitagliptin | 1.29 | 1.68
Metformin HCl | 1000 mg [Multiple dose.] twice daily for 14 days | 50 mg twice daily for 7 days | Sitagliptin | 1.02 [AUC0-12hr.] | 1.05

Metformin

Table 7: Effect of Metformin on Systemic Exposure of Coadministered Drugs
Coadministered Drug | Dose of Coadministered Drug [All doses administered as single dose unless otherwise specified] | Dose of Metformin HCl | Geometric Mean Ratio (ratio with/without metformin) No Effect = 1.00
 |  |  |  | AUC [AUC is reported as AUC0-∞ unless otherwise specified] | Cmax
Cimetidine | 400 mg | 850 mg | Cimetidine | 0.95 [AUC0-24hr] | 1.01
Glyburide | 5 mg | 500 mg [GLUMETZA (metformin HCl extended-release tablets) 500 mg] | Glyburide | 0.78 [Ratio of arithmetic means, p value of difference <0.05] | 0.63
Furosemide | 40 mg | 850 mg | Furosemide | 0.87 | 0.69
Nifedipine | 10 mg | 850 mg | Nifedipine | 1.10 | 1.08
Propranolol | 40 mg | 850 mg | Propranolol | 1.01 | 0.94
Ibuprofen | 400 mg | 850 mg | Ibuprofen | 0.97 [Ratio of arithmetic means] | 1.01

Table 8: Effect of Coadministered Drugs on Systemic Exposure of Metformin
Coadministered Drug | Dose of Coadministered Drug [All doses administered as single dose unless otherwise specified] | Dose of Metformin HCl | Geometric Mean Ratio (ratio with/without coadministered drug) No Effect = 1.00
 |  |  |  | AUC [AUC is reported as AUC0-∞ unless otherwise specified] | Cmax
Glyburide | 5 mg | 500 mg [GLUMETZA (metformin HCl extended-release tablets) 500 mg] | Metformin | 0.98 [Ratio of arithmetic means] | 0.99
Furosemide | 40 mg | 850 mg | Metformin | 1.09 | 1.22
Nifedipine | 10 mg | 850 mg | Metformin | 1.16 | 1.21
Propranolol | 40 mg | 850 mg | Metformin | 0.90 | 0.94
Ibuprofen | 400 mg | 850 mg | Metformin | 1.05 | 1.07
Drugs that are eliminated by renal tubular secretion may increase the accumulation of metformin. [See Warnings and Precautions (5.1) and Drug Interactions (7).]
Cimetidine | 400 mg | 850 mg | Metformin | 1.40 | 1.61
Carbonic anhydrase inhibitors may cause metabolic acidosis [See Warnings and Precautions (5.1) and Drug Interactions (7).]
Topiramate | 100 mg [Steady state 100 mg Topiramate every 12 hr + metformin HCl 500 mg every 12 hr. AUC = AUC0-12hr] | 500 mg | Metformin | 1.25 | 1.17

13 NONCLINICAL TOXICOLOGY

13.1 Carcinogenesis, Mutagenesis, Impairment of Fertility

JANUMET XR

No animal studies have been conducted with the combined products in JANUMET XR to evaluate carcinogenesis, mutagenesis or impairment of fertility. The following data are based on the findings in studies with sitagliptin and metformin individually.

Sitagliptin

A two-year carcinogenicity study was conducted in male and female rats given oral doses of sitagliptin of 50, 150, and 500 mg/kg/day. There was an increased incidence of combined liver adenoma/carcinoma in males and females and of liver carcinoma in females at 500 mg/kg. This dose results in exposures approximately 60 times the human exposure at the maximum recommended daily adult human dose (MRHD) of 100 mg/day based on AUC comparisons. Liver tumors were not observed at 150 mg/kg, approximately 20 times the human exposure at the MRHD. A two-year carcinogenicity study was conducted in male and female mice given oral doses of sitagliptin of 50, 125, 250, and 500 mg/kg/day. There was no increase in the incidence of tumors in any organ up to 500 mg/kg, approximately 70 times human exposure at the MRHD. Sitagliptin was not mutagenic or clastogenic with or without metabolic activation in the Ames bacterial mutagenicity assay, a Chinese hamster ovary (CHO) chromosome aberration assay, an in vitro cytogenetics assay in CHO, an in vitro rat hepatocyte DNA alkaline elution assay, and an in vivo micronucleus assay.

In rat fertility studies with oral gavage doses of 125, 250, and 1000 mg/kg, males were treated for 4 weeks prior to mating, during mating, up to scheduled termination (approximately 8 weeks total), and females were treated 2 weeks prior to mating through gestation day 7. No adverse effect on fertility was observed at 125 mg/kg (approximately 12 times human exposure at the MRHD of 100 mg/day based on AUC comparisons). At higher doses, nondose-related increased resorptions in females were observed (approximately 25 and 100 times human exposure at the MRHD based on AUC comparison).

Metformin

Long-term carcinogenicity studies have been performed in Sprague Dawley rats at doses of 150, 300, and 450 mg/kg/day in males and 150, 450, 900, and 1200 mg/kg/day in females. These doses are approximately 2, 4, and 8 times in males, and 3, 7, 12, and 16 times in females of the maximum recommended human daily dose of 2000 mg based on body surface area comparisons. No evidence of carcinogenicity with metformin was found in either male or female rats. A carcinogenicity study was also performed in Tg.AC transgenic mice at doses up to 2000 mg applied dermally. No evidence of carcinogenicity was observed in male or female mice.

Genotoxicity assessments in the Ames test, gene mutation test (mouse lymphoma cells), chromosomal aberrations test (human lymphocytes) and in vivo mouse micronucleus tests were negative. Fertility of male or female rats was not affected by metformin when administered at doses up to 600 mg/kg/day, which is approximately 3 times the maximum recommended human daily dose based on body surface area comparisons.

14 CLINICAL STUDIES

The coadministration of sitagliptin and metformin immediate-release has been studied in patients with type 2 diabetes inadequately controlled on diet and exercise and in combination with other antidiabetic medications.

There have been no clinical efficacy or safety studies conducted with JANUMET XR to characterize its effect on hemoglobin A1c (A1C) reduction. Bioequivalence of JANUMET XR tablets with coadministered sitagliptin and extended-release metformin tablets has been demonstrated for all tablet strengths [see Clinical Pharmacology (12.3)].

Metformin Extended-Release Compared to Metformin Immediate-Release in Patients with Type 2 Diabetes

In a multicenter, randomized, double-blind, active-controlled, dose-ranging, parallel group trial extended-release metformin HCl 1500 mg once daily, extended-release metformin HCl 1500 mg per day in divided doses (500 mg in the morning and 1000 mg in the evening), and extended-release metformin HCl 2000 mg once daily were compared to immediate-release metformin HCl 1500 mg per day in divided doses (500 mg in the morning and 1000 mg in the evening). This trial enrolled patients (n = 338) who were newly diagnosed with diabetes, patients treated only with diet and exercise, patients treated with a single anti-diabetic medication (sulfonylureas, alpha-glucosidase inhibitors, thiazolidinediones, or meglitinides), and patients (n = 368) receiving metformin HCl up to 1500 mg/day plus a sulfonylurea at a dose equal to or less than one-half the maximum dose. Patients who were enrolled on monotherapy or combination antidiabetic therapy underwent a 6-week washout. Patients randomized to extended-release metformin HCl began titration from 1000 mg/day up to their assigned treatment dose over 3 weeks. Patients randomized to immediate-release metformin HCl initiated 500 mg twice daily for 1 week followed by 500 mg with breakfast and 1000 mg with dinner for the second week. The 3-week treatment period was followed by an additional 21-week period at the randomized dose. For HbA1c and fasting plasma glucose, each of the extended-release metformin regimens was at least as effective as immediate-release metformin. Additionally, once daily dosing of extended-release metformin was as effective as twice daily dosing of the immediate-release metformin formulation.

Sitagliptin and Metformin Immediate-Release Coadministration in Patients with Type 2 Diabetes Inadequately Controlled on Diet and Exercise

A total of 1091 patients with type 2 diabetes and inadequate glycemic control on diet and exercise participated in a 24-week, randomized, double-blind, placebo-controlled factorial study designed to assess the efficacy of sitagliptin and metformin immediate-release coadministration. Patients on an antihyperglycemic agent (N=541) underwent a diet, exercise, and drug washout period of up to 12 weeks duration. After the washout period, patients with inadequate glycemic control (A1C 7.5% to 11%) were randomized after completing a 2-week single-blind placebo run-in period. Patients not on antihyperglycemic agents at study entry (N=550) with inadequate glycemic control (A1C 7.5% to 11%) immediately entered the 2-week single-blind placebo run-in period and then were randomized. Approximately equal numbers of patients were randomized to receive placebo, 100 mg of sitagliptin once daily, 500 mg or 1000 mg of metformin HCl immediate-release twice daily, or 50 mg of sitagliptin twice daily in combination with 500 mg or 1000 mg of metformin HCl immediate-release twice daily. Patients who failed to meet specific glycemic goals during the study were treated with glyburide (glibenclamide) rescue.

Sitagliptin and metformin immediate-release coadministration provided significant improvements in A1C, FPG, and 2-hour PPG compared to placebo, to metformin immediate-release alone, and to sitagliptin alone (Table 9, Figure 1). For patients not on an antihyperglycemic agent at study entry, mean reductions from baseline in A1C were: sitagliptin 100 mg once daily, -1.1%; metformin HCl immediate-release 500 mg bid, -1.1%; metformin HCl immediate-release 1000 mg bid, -1.2%; sitagliptin 50 mg bid with metformin HCl immediate-release 500 mg bid, -1.6%; sitagliptin 50 mg bid with metformin HCl immediate-release 1000 mg bid, -1.9%; and for patients receiving placebo, -0.2%. Lipid effects were generally neutral. The decrease in body weight in the groups given sitagliptin in combination with metformin immediate-release was similar to that in the groups given metformin alone or placebo.

Table 9: Glycemic Parameters at Final Visit (24-Week Study) for Sitagliptin and Metformin Immediate-Release, Alone and in Combination in Patients with Type 2 Diabetes Inadequately Controlled on Diet and Exercise [Intent-to-treat population using last observation on study prior to glyburide (glibenclamide) rescue therapy.]
 | Placebo | Sitagliptin 100 mg once daily | Metformin HCl Immediate-Release 500 mg twice daily | Metformin HCl Immediate-Release 1000 mg twice daily | Sitagliptin 50 mg bid + Metformin HCl Immediate-Release 500 mg twice daily | Sitagliptin 50 mg bid + Metformin HCl Immediate-Release 1000 mg twice daily
A1C (%) | N = 165 | N = 175 | N = 178 | N = 177 | N = 183 | N = 178
Baseline (mean) | 8.7 | 8.9 | 8.9 | 8.7 | 8.8 | 8.8
Change from baseline (adjusted mean [Least squares means adjusted for prior antihyperglycemic therapy status and baseline value.]) | 0.2 | -0.7 | -0.8 | -1.1 | -1.4 | -1.9
Difference from placebo (adjusted mean) (95% CI) |  | -0.8 [p<0.001 compared to placebo.] (-1.1, -0.6) | -1.0 (-1.2, -0.8) | -1.3 (-1.5, -1.1) | -1.6 (-1.8, -1.3) | -2.1 (-2.3, -1.8)
Patients (%) achieving A1C <7% | 15 (9%) | 35 (20%) | 41 (23%) | 68 (38%) | 79 (43%) | 118 (66%)
% Patients receiving rescue medication | 32 | 21 | 17 | 12 | 8 | 2
FPG (mg/dL) | N = 169 | N = 178 | N = 179 | N = 179 | N = 183 | N = 180
Baseline (mean) | 196 | 201 | 205 | 197 | 204 | 197
Change from baseline (adjusted mean) | 6 | -17 | -27 | -29 | -47 | -64
Difference from placebo (adjusted mean) (95% CI) |  | -23 (-33, -14) | -33 (-43, -24) | -35 (-45, -26) | -53 (-62, -43) | -70 (-79, -60)
2-hour PPG (mg/dL) | N = 129 | N = 136 | N = 141 | N = 138 | N = 147 | N = 152
Baseline (mean) | 277 | 285 | 293 | 283 | 292 | 287
Change from baseline (adjusted mean) | 0 | -52 | -53 | -78 | -93 | -117
Difference from placebo (adjusted mean) (95% CI) |  | -52 (-67, -37) | -54 (-69, -39) | -78 (-93, -63) | -93 (-107, -78) | -117 (-131, -102)

Figure 1: Mean Change from Baseline for A1C (%) over 24 Weeks with Sitagliptin and Metformin Immediate-Release, Alone and in Combination in Patients with Type 2 Diabetes Inadequately Controlled with Diet and Exercise [The Completers Population: least squares means adjusted for prior antihyperglycemic therapy and baseline value.]

Initial combination therapy or maintenance of combination therapy should be individualized and are left to the discretion of the health care provider.

Sitagliptin Add-on Therapy in Patients with Type 2 Diabetes Inadequately Controlled on Metformin Immediate-Release Alone

A total of 701 patients with type 2 diabetes participated in a 24-week, randomized, double-blind, placebo-controlled study designed to assess the efficacy of sitagliptin in combination with metformin immediate-release. Patients already on metformin HCl immediate-release (N=431) at a dose of at least 1500 mg per day were randomized after completing a 2-week, single-blind placebo run-in period. Patients on metformin immediate-release and another antihyperglycemic agent (N=229) and patients not on any antihyperglycemic agents (off therapy for at least 8 weeks, N=41) were randomized after a run-in period of approximately 10 weeks on metformin HCl immediate-release (at a dose of at least 1500 mg per day) in monotherapy. Patients were randomized to the addition of either 100 mg of sitagliptin or placebo, administered once daily. Patients who failed to meet specific glycemic goals during the studies were treated with pioglitazone rescue.

In combination with metformin immediate-release, sitagliptin provided significant improvements in A1C, FPG, and 2-hour PPG compared to placebo with metformin immediate-release (Table 10). Rescue glycemic therapy was used in 5% of patients treated with sitagliptin 100 mg and 14% of patients treated with placebo. A similar decrease in body weight was observed for both treatment groups.

Table 10: Glycemic Parameters at Final Visit (24-Week Study) of Sitagliptin as Add-on Combination Therapy with Metformin Immediate-Release [Intent-to-treat population using last observation on study prior to pioglitazone rescue therapy.]
 | Sitagliptin 100 mg once daily + Metformin Immediate-Release | Placebo + Metformin Immediate-Release
A1C (%) | N = 453 | N = 224
Baseline (mean) | 8.0 | 8.0
Change from baseline (adjusted mean [Least squares means adjusted for prior antihyperglycemic therapy and baseline value.]) | -0.7 | -0.0
Difference from placebo + metformin immediate- release (adjusted mean) (95% CI) | -0.7 [p<0.001 compared to placebo + metformin.] (-0.8, -0.5)
Patients (%) achieving A1C <7% | 213 (47%) | 41 (18%)
FPG (mg/dL) | N = 454 | N = 226
Baseline (mean) | 170 | 174
Change from baseline (adjusted mean) | -17 | 9
Difference from placebo + metformin immediate- release (adjusted mean) (95% CI) | -25 (-31, -20)
2-hour PPG (mg/dL) | N = 387 | N = 182
Baseline (mean) | 275 | 272
Change from baseline (adjusted mean) | -62 | -11
Difference from placebo + metformin immediate- release (adjusted mean) (95% CI) | -51 (-61, -41)

Sitagliptin Add-on Therapy in Patients with Type 2 Diabetes Inadequately Controlled on the Combination of Metformin Immediate-Release and Glimepiride

A total of 441 patients with type 2 diabetes participated in a 24-week, randomized, double-blind, placebo-controlled study designed to assess the efficacy of sitagliptin in combination with glimepiride, with or without metformin immediate-release. Patients entered a run-in treatment period on glimepiride (≥4 mg per day) alone or glimepiride in combination with metformin HCl immediate-release (≥1500 mg per day). After a dose-titration and dose-stable run-in period of up to 16 weeks and a 2-week placebo run-in period, patients with inadequate glycemic control (A1C 7.5% to 10.5%) were randomized to the addition of either 100 mg of sitagliptin or placebo, administered once daily. Patients who failed to meet specific glycemic goals during the studies were treated with pioglitazone rescue.

Patients receiving sitagliptin with metformin immediate-release and glimepiride had significant improvements in A1C and FPG compared to patients receiving placebo with metformin immediate-release and glimepiride (Table 11), with mean reductions from baseline relative to placebo in A1C of -0.9% and in FPG of -21 mg/dL. Rescue therapy was used in 8% of patients treated with add-on sitagliptin 100 mg and 29% of patients treated with add-on placebo. The patients treated with add-on sitagliptin had a mean increase in body weight of 1.1 kg vs. add-on placebo (+0.4 kg vs. -0.7 kg). In addition, add-on sitagliptin resulted in an increased rate of hypoglycemia compared to add-on placebo. [See Warnings and Precautions (5.6); Adverse Reactions (6.1).]

Table 11: Glycemic Parameters at Final Visit (24-Week Study) for Sitagliptin in Combination with Metformin Immediate-Release and Glimepiride [Intent-to-treat population using last observation on study prior to pioglitazone rescue therapy.]
 | Sitagliptin 100 mg + Metformin Immediate-Release and Glimepiride | Placebo + Metformin Immediate-Release and Glimepiride
A1C (%) | N = 115 | N = 105
Baseline (mean) | 8.3 | 8.3
Change from baseline (adjusted mean [Least squares means adjusted for prior antihyperglycemic therapy status and baseline value.]) | -0.6 | 0.3
Difference from placebo (adjusted mean) (95% CI) | -0.9 [p<0.001 compared to placebo.] (-1.1, -0.7)
Patients (%) achieving A1C <7% | 26 (23%) | 1 (1%)
FPG (mg/dL) | N = 115 | N = 109
Baseline (mean) | 179 | 179
Change from baseline (adjusted mean) | -8 | 13
Difference from placebo (adjusted mean) (95% CI) | -21 (-32, -10)

Sitagliptin Add-on Therapy in Patients with Type 2 Diabetes Inadequately Controlled on the Combination of Metformin Immediate-Release and Rosiglitazone

A total of 278 patients with type 2 diabetes participated in a 54-week, randomized, double-blind, placebo-controlled study designed to assess the efficacy of sitagliptin in combination with metformin immediate-release and rosiglitazone. Patients on dual therapy with metformin HCl immediate-release ≥1500 mg/day and rosiglitazone ≥4 mg/day or with metformin HCl immediate-release ≥1500 mg/day and pioglitazone ≥30 mg/day (switched to rosiglitazone ≥4 mg/day) entered a dose-stable run-in period of 6 weeks. Patients on other dual therapy were switched to metformin HCl immediate-release ≥1500 mg/day and rosiglitazone ≥4 mg/day in a dose titration/stabilization run-in period of up to 20 weeks in duration. After the run-in period, patients with inadequate glycemic control (A1C 7.5% to 11%) were randomized 2:1 to the addition of either 100 mg of sitagliptin or placebo, administered once daily. Patients who failed to meet specific glycemic goals during the studies were treated with glipizide (or other sulfonylurea) rescue. The primary time point for evaluation of glycemic parameters was Week 18.

In combination with metformin immediate-release and rosiglitazone, sitagliptin provided significant improvements in A1C, FPG, and 2-hour PPG compared to placebo with metformin immediate-release and rosiglitazone (Table 12) at Week 18. At Week 54, mean reduction in A1C was -1.0% for patients treated with sitagliptin and -0.3% for patients treated with placebo in an analysis based on the intent-to-treat population. Rescue therapy was used in 18% of patients treated with sitagliptin 100 mg and 40% of patients treated with placebo. There was no significant difference between sitagliptin and placebo in body weight change.

Table 12: Glycemic Parameters at Week 18 for Sitagliptin in Add-on Combination Therapy with Metformin Immediate-Release and Rosiglitazone [Intent-to-treat population using last observation on study prior to glipizide (or other sulfonylurea) rescue therapy.]
 | Week 18
 | Sitagliptin 100 mg + Metformin Immediate-Release + Rosiglitazone | Placebo + Metformin Immediate-Release + Rosiglitazone
A1C (%) | N = 176 | N = 93
Baseline (mean) | 8.8 | 8.7
Change from baseline (adjusted mean [Least squares means adjusted for prior antihyperglycemic therapy status and baseline value.]) | -1.0 | -0.4
Difference from placebo + rosiglitazone + metformin immediate-release (adjusted mean) (95% CI) | -0.7 [p<0.001 compared to placebo + metformin + rosiglitazone.] (-0.9, -0.4)
Patients (%) achieving A1C <7% | 39 (22%) | 9 (10%)
FPG (mg/dL) | N = 179 | N = 94
Baseline (mean) | 181 | 182
Change from baseline (adjusted mean) | -30 | -11
Difference from placebo + rosiglitazone + metformin immediate-release (adjusted mean) (95% CI) | -18 (-26, -10)
2-hour PPG (mg/dL) | N = 152 | N = 80
Baseline (mean) | 256 | 248
Change from baseline (adjusted mean) | -59 | -21
Difference from placebo + rosiglitazone + metformin immediate-release (adjusted mean) (95% CI) | -39 (-51, -26)

Sitagliptin Add-on Therapy in Patients with Type 2 Diabetes Inadequately Controlled on the Combination of Metformin Immediate-Release and Insulin

A total of 641 patients with type 2 diabetes participated in a 24-week, randomized, double-blind, placebo-controlled study designed to assess the efficacy of sitagliptin as add-on to insulin therapy. Approximately 75% of patients were also taking metformin immediate-release. Patients entered a 2-week, single-blind run-in treatment period on pre-mixed, long-acting, or intermediate-acting insulin, with or without metformin HCl immediate-release (≥1500 mg per day). Patients using short-acting insulins were excluded unless the short-acting insulin was administered as part of a pre-mixed insulin. After the run-in period, patients with inadequate glycemic control (A1C 7.5% to 11%) were randomized to the addition of either 100 mg of sitagliptin (N=229) or placebo (N=233), administered once daily. Patients were on a stable dose of insulin prior to enrollment with no changes in insulin dose permitted during the run-in period. Patients who failed to meet specific glycemic goals during the double-blind treatment period were to have uptitration of the background insulin dose as rescue therapy.

Among patients also receiving metformin immediate-release, the median daily insulin (pre-mixed, intermediate or long acting) dose at baseline was 40 units in the sitagliptin-treated patients and 42 units in the placebo-treated patients. The median change from baseline in daily dose of insulin was zero for both groups at the end of the study. Patients receiving sitagliptin with metformin immediate-release and insulin had significant improvements in A1C, FPG and 2-hour PPG compared to patients receiving placebo with metformin immediate-release and insulin (Table 13). The adjusted mean change from baseline in body weight was -0.3 kg in patients receiving sitagliptin with metformin immediate-release and insulin and -0.2 kg in patients receiving placebo with metformin immediate-release and insulin. There was an increased rate of hypoglycemia in patients treated with sitagliptin. [See Warnings and Precautions (5.6); Adverse Reactions (6.1).]

Table 13: Glycemic Parameters at Final Visit (24-Week Study) for Sitagliptin as Add-on Combination Therapy with Metformin Immediate-Release and Insulin [Intent-to-treat population using last observation on study prior to rescue therapy.]
 | Sitagliptin 100 mg + Metformin Immediate-Release + Insulin | Placebo + Metformin Immediate-Release + Insulin
A1C (%) | N = 223 | N = 229
Baseline (mean) | 8.7 | 8.6
Change from baseline (adjusted mean [Least squares means adjusted for insulin use at the screening visit, type of insulin used at the screening visit (pre-mixed vs. non pre-mixed [intermediate- or long-acting]), and baseline value.] , [Treatment by insulin stratum interaction was not significant (p>0.10).]) | -0.7 | -0.1
Difference from placebo (adjusted mean) (95% CI) | -0.5 [p<0.001 compared to placebo.] (-0.7, -0.4)
Patients (%) achieving A1C <7% | 32 (14%) | 12 (5%)
FPG (mg/dL) | N = 225 | N = 229
Baseline (mean) | 173 | 176
Change from baseline (adjusted mean) | -22 | -4
Difference from placebo (adjusted mean) (95% CI) | -18 (-28, -8.4)
2-hour PPG (mg/dL) | N = 182 | N = 189
Baseline (mean) | 281 | 281
Change from baseline (adjusted mean) | -39 | 1
Difference from placebo (adjusted mean) (95% CI) | -40 (-53, -28)

Maintenance of Sitagliptin During Initiation and Titration of Insulin Glargine

A total of 746 patients with type 2 diabetes (mean baseline HbA1C 8.8%, disease duration 10.8 years) participated in a 30-week, randomized, double-blind, placebo-controlled study to assess the efficacy and safety of continuing sitagliptin during the initiation and uptitration of insulin glargine. Patients who were on a stable dose of metformin HCl (≥1500 mg/day) in combination with a DPP-4 inhibitor and/or sulfonylurea but with inadequate glycemic control (A1C 7.5% to 11%) were enrolled in the study. Those on metformin and sitagliptin (100 mg/day) directly entered the double-blind treatment period; those on another DPP-4 inhibitor and/or on a sulfonylurea entered a 4-8 week run-in period in which they were maintained on metformin and switched to sitagliptin (100 mg); other DPP-4 inhibitors and sulfonylureas were discontinued. At randomization patients were randomized either to continue sitagliptin or to discontinue sitagliptin and switch to a matching placebo. On the day of randomization, insulin glargine was initiated at a dose of 10 units subcutaneously in the evening. Patients were instructed to uptitrate their insulin dose in the evening based on fasting blood glucose measurements to achieve a target of 72-100 mg/dL.

At 30 weeks, the mean reduction in A1C was greater in the sitagliptin group than in the placebo group (Table 14). At the end of the trial, 27.3% of patients in the sitagliptin group and 27.3% in the placebo group had a fasting plasma glucose (FPG) in the target range; there was no significant difference in insulin dose between arms.

Table 14: Change from Baseline in A1C and FPG at Week 30 in the Maintenance of Sitagliptin During Initiation and Titration of Insulin Glargine Study
 | Sitagliptin 100 mg+Metformin+ Insulin Glargine | Placebo+Metformin+ Insulin Glargine
A1C (%) | N = 373 [N is the number of randomized and treated patients.] | N = 370
Baseline (mean) | 8.8 | 8.8
Week 30 (mean) | 6.9 | 7.3
Change from baseline (adjusted mean) [Analysis of Covariance including all post-baseline data regardless of rescue or treatment discontinuation. Model estimates calculated using multiple imputation to model washout of the treatment effect using placebo data for all subjects having missing Week 30 data.] | -1.9 | -1.4
Difference from placebo (adjusted mean) (95% CI) | -0.4 (-0.6, -0.3) [p<0.001 compared to placebo.]
Patients (%) with A1C <7% | 202 (54.2%) | 131 (35.4%)
FPG (mg/dL) | N = 373 | N = 370
Baseline (mean) | 199 | 201
Week 30 (mean) | 118 | 123
Change from baseline (adjusted mean) | -81 | -76

Sitagliptin Add-on Therapy vs. Glipizide Add-on Therapy in Patients with Type 2 Diabetes Inadequately Controlled on Metformin Immediate-Release

The efficacy of sitagliptin was evaluated in a 52-week, double-blind, glipizide-controlled noninferiority trial in patients with type 2 diabetes. Patients not on treatment or on other antihyperglycemic agents entered a run-in treatment period of up to 12 weeks duration with metformin HCl immediate-release monotherapy (dose of ≥1500 mg per day) which included washout of medications other than metformin immediate-release, if applicable. After the run-in period, those with inadequate glycemic control (A1C 6.5% to 10%) were randomized 1:1 to the addition of sitagliptin 100 mg once daily or glipizide for 52 weeks. Patients receiving glipizide were given an initial dosage of 5 mg/day and then electively titrated over the next 18 weeks to a maximum dosage of 20 mg/day as needed to optimize glycemic control. Thereafter, the glipizide dose was to be kept constant, except for down-titration to prevent hypoglycemia. The mean dose of glipizide after the titration period was 10 mg.

After 52 weeks, sitagliptin and glipizide had similar mean reductions from baseline in A1C in the intent-to-treat analysis (Table 15). These results were consistent with the per protocol analysis (Figure 2). A conclusion in favor of the non-inferiority of sitagliptin to glipizide may be limited to patients with baseline A1C comparable to those included in the study (over 70% of patients had baseline A1C <8% and over 90% had A1C <9%).

Table 15: Glycemic Parameters in a 52-Week Study Comparing Sitagliptin to Glipizide as Add-On Therapy in Patients Inadequately Controlled on Metformin Immediate-Release (Intent-to-Treat Population) [The intent-to-treat analysis used the patients' last observation in the study prior to discontinuation.]
 | Sitagliptin 100 mg + Metformin Immediate-Release | Glipizide + Metformin Immediate-Release
A1C (%) | N = 576 | N = 559
Baseline (mean) | 7.7 | 7.6
Change from baseline (adjusted mean [Least squares means adjusted for prior antihyperglycemic therapy status and baseline A1C value.]) | -0.5 | -0.6
FPG (mg/dL) | N = 583 | N = 568
Baseline (mean) | 166 | 164
Change from baseline (adjusted mean) | -8 | -8

Figure 2: Mean Change from Baseline for A1C (%) Over 52 Weeks in a Study Comparing Sitagliptin to Glipizide as Add-On Therapy in Patients Inadequately Controlled on Metformin Immediate-Release (Per Protocol Population) [The per protocol population (mean baseline A1C of 7.5%) included patients without major protocol violations who had observations at baseline and at Week 52.]

The incidence of hypoglycemia in the sitagliptin group (4.9%) was significantly (p<0.001) lower than that in the glipizide group (32.0%). Patients treated with sitagliptin exhibited a significant mean decrease from baseline in body weight compared to a significant weight gain in patients administered glipizide (-1.5 kg vs. +1.1 kg).

16 HOW SUPPLIED/STORAGE AND HANDLING

Tablets supplied as follows:

Contents | Description | How Supplied | NDC
50 mg sitagliptin and 500 mg metformin HCl extended-release | light blue, bi-convex oval, film-coated tablets with “78” debossed on one side | unit-of-use bottles of 60 | NDC 0006-0078-61
50 mg sitagliptin and 500 mg metformin HCl extended-release | light blue, bi-convex oval, film-coated tablets with “78” debossed on one side | unit-of-use bottles of 180 | NDC 0006-0078-62
50 mg sitagliptin and 500 mg metformin HCl extended-release | light blue, bi-convex oval, film-coated tablets with “78” debossed on one side | bulk bottles of 1000 | NDC 0006-0078-82
50 mg sitagliptin and 1000 mg metformin HCl extended-release | light green, bi-convex oval, film-coated tablets with “80” debossed on one side | unit-of-use bottles of 60 | NDC 0006-0080-61
50 mg sitagliptin and 1000 mg metformin HCl extended-release | light green, bi-convex oval, film-coated tablets with “80” debossed on one side | unit-of-use bottles of 180 | NDC 0006-0080-62
50 mg sitagliptin and 1000 mg metformin HCl extended-release | light green, bi-convex oval, film-coated tablets with “80” debossed on one side | bulk bottles of 1000 | NDC 0006-0080-82
100 mg sitagliptin and 1000 mg metformin HCl extended-release | blue, bi-convex oval, film-coated tablets with “81” debossed on one side | unit-of-use bottles of 30 | NDC 0006-0081-31
100 mg sitagliptin and 1000 mg metformin HCl extended-release | blue, bi-convex oval, film-coated tablets with “81” debossed on one side | unit-of-use bottles of 90 | NDC 0006-0081-54
100 mg sitagliptin and 1000 mg metformin HCl extended-release | blue, bi-convex oval, film-coated tablets with “81” debossed on one side | bulk bottles of 1000 | NDC 0006-0081-82

STORAGE AND HANDLING

Store at 20-25°C (68-77°F), excursions permitted to 15-30°C (59-86°F). [See USP Controlled Room Temperature.] Store in a dry place with cap tightly closed. When container is subdivided, dispense into a USP tightly closed, moisture-resistant container.

17 PATIENT COUNSELING INFORMATION

Advise the patient to read the FDA-approved patient labeling (Medication Guide).

Lactic Acidosis

Explain the risks of lactic acidosis, its symptoms, and conditions that predispose to its development. Advise patients to discontinue JANUMET XR immediately and to promptly notify their healthcare provider if unexplained hyperventilation, myalgias, malaise, unusual somnolence or other nonspecific symptoms occur. Counsel patients against excessive alcohol intake and inform patients about the importance of regular testing of renal function while receiving JANUMET XR. Instruct patients to inform their doctor that they are taking JANUMET XR prior to any surgical or radiological procedure, as temporary discontinuation may be required [see Warnings and Precautions (5.1)].

Pancreatitis

Inform patients that acute pancreatitis has been reported during postmarketing use of JANUMET XR. Inform patients that persistent severe abdominal pain, sometimes radiating to the back, which may or may not be accompanied by vomiting, is the hallmark symptom of acute pancreatitis. Instruct patients to promptly discontinue JANUMET XR and contact their physician if persistent severe abdominal pain occurs [see Warnings and Precautions (5.2)].

Heart Failure

Inform patients of the signs and symptoms of heart failure. Before initiating JANUMET XR, ask patients about a history of heart failure or other risk factors for heart failure including moderate to severe renal impairment. Instruct patients to contact their health care provider as soon as possible if they experience symptoms of heart failure, including increasing shortness of breath, rapid increase in weight or swelling of the feet [see Warnings and Precautions (5.3)].

Vitamin B12 Deficiency

Inform patients about the importance of regular monitoring of hematological parameters while receiving JANUMET XR [see Warnings and Precautions (5.5)].

Hypoglycemia

Inform patients that the incidence of hypoglycemia is increased when sitagliptin with or without metformin is added to an insulin secretagogue (e.g., sulfonylurea) or insulin therapy. Explain to patients receiving JANUMET XR in combination with these medications the risks of hypoglycemia, its symptoms and treatment and conditions that predispose to its development [see Warnings and Precautions (5.6)].

Hypersensitivity Reactions

Inform patients that allergic reactions have been reported during postmarketing use of sitagliptin, one of the components of JANUMET XR. If symptoms of allergic reactions (including rash, hives, and swelling of the face, lips, tongue, and throat that may cause difficulty in breathing or swallowing) occur, patients must stop taking JANUMET XR and seek medical advice promptly.

Severe and Disabling Arthralgia

Inform patients that severe and disabling joint pain may occur with this class of drugs. The time to onset of symptoms can range from one day to years. Instruct patients to seek medical advice if severe joint pain occurs [see Warnings and Precautions (5.8)].

Bullous Pemphigoid

Inform patients that bullous pemphigoid may occur with this class of drugs. Instruct patients to seek medical advice if blisters or erosions occur [see Warnings and Precautions (5.9)].

Administration Instructions

Inform patients that the tablets must be swallowed whole and never split, crushed or chewed.

Incompletely Dissolved Tablets in Feces

Inform patients that incompletely dissolved JANUMET XR tablets may be eliminated in the feces. Tell patients that, if they repeatedly see tablets in feces, they should report this finding to their health care provider. Assess adequacy of glycemic control if a patient reports repeatedly observing tablets in feces.

Females of Reproductive Age:

Inform females that treatment with JANUMET XR may result in ovulation in some premenopausal anovulatory women which may lead to unintended pregnancy [see Use in Specific Populations (8.3)].

Distributed by: Merck Sharp & Dohme LLC
Rahway, NJ 07065, USA

For patent information: www.msd.com/research/patent

Copyright © 2012-2022 Merck & Co., Inc., Rahway, NJ, USA, and its affiliates.
All rights reserved.

uspi-mk0431a-xrt-2207r020

Medication Guide
JANUMET® XR (JAN-you-met XR)
(sitagliptin and metformin hydrochloride extended-release)
tablets, for oral use

Read this Medication Guide carefully before you start taking JANUMET XR and each time you get a refill. There may be new information. This information does not take the place of talking with your doctor about your medical condition or your treatment. If you have any questions about JANUMET XR, ask your doctor or pharmacist.

What is the most important information I should know about JANUMET XR?
JANUMET XR can cause serious side effects, including:

1. Lactic Acidosis. Metformin, one of the medicines in JANUMET XR, can cause a rare but serious condition called lactic acidosis (a buildup of an acid in the blood) that can cause death. Lactic acidosis is a medical emergency and must be treated in the hospital.

Stop taking JANUMET XR and call your doctor right away if you have any of the following symptoms, which could be signs of lactic acidosis:

- you feel cold in your hands or feet
- you feel dizzy or lightheaded
- you have a slow or irregular heartbeat
- you feel very weak or tired
- you have unusual (not normal) muscle pain
- you have trouble breathing
- you feel sleepy or drowsy
- you have stomach pains, nausea or vomiting

Most people who have had lactic acidosis with metformin have other things that, combined with the metformin, led to the lactic acidosis. Tell your doctor if you have any of the following, because you have a higher chance for getting lactic acidosis with JANUMET XR if you:

- have severe kidney problems or your kidneys are affected by certain x-ray tests that use injectable dye
- have liver problems
- drink alcohol very often, or drink a lot of alcohol in short-term "binge" drinking
- get dehydrated (lose a large amount of body fluids). This can happen if you are sick with a fever, vomiting, or diarrhea. Dehydration can also happen when you sweat a lot with activity or exercise and do not drink enough fluids.
- have surgery
- have a heart attack, severe infection, or stroke
- are 65 years of age or older

The best way to keep from having a problem with lactic acidosis from metformin is to tell your doctor if you have any of the problems in the list above. Your doctor may decide to stop your JANUMET XR for a while if you have any of these things.

JANUMET XR can have other serious side effects. See "What are the possible side effects of JANUMET XR?"

2. Pancreatitis (inflammation of the pancreas) which may be severe and lead to death. Certain medical problems make you more likely to get pancreatitis.

Before you start taking JANUMET XR, tell your doctor if you have ever had:

  - pancreatitis
  - stones in your gallbladder (gallstones)
  - a history of alcoholism
  - high blood triglyceride levels

Stop taking JANUMET XR and call your doctor right away if you have pain in your stomach area (abdomen) that is severe and will not go away. The pain may be felt going from your abdomen through to your back. The pain may happen with or without vomiting. These may be symptoms of pancreatitis.

3. Heart failure. Heart failure means that your heart does not pump blood well enough.

Before you start taking JANUMET XR, tell your doctor if you have ever had heart failure or have problems with your kidneys. Contact your doctor right away if you have any of the following symptoms:

- increasing shortness of breath or trouble breathing, especially when you lie down
- swelling or fluid retention, especially in the feet, ankles or legs
- an unusually fast increase in weight
- unusual tiredness

These may be symptoms of heart failure.

What is JANUMET XR?

- JANUMET XR is a prescription medicine that contains 2 prescription diabetes medicines, sitagliptin (JANUVIA) and extended-release metformin hydrochloride. JANUMET XR can be used along with diet and exercise to lower blood sugar in adults with type 2 diabetes.
- JANUMET XR is not for people with type 1 diabetes.
- If you have had pancreatitis (inflammation of the pancreas) in the past, it is not known if you have a higher chance of getting pancreatitis while you take JANUMET XR.
- The safety and effectiveness of JANUMET XR have not been established in pediatric patients.

Who should not take JANUMET XR?
Do not take JANUMET XR if you:

- have severe kidney problems.
- have diabetic ketoacidosis.
- are allergic to any of the ingredients in JANUMET XR. See the end of this Medication Guide for a complete list of ingredients in JANUMET XR.

Symptoms of a serious allergic reaction to JANUMET XR may include rash, raised red patches on your skin (hives) or swelling of the face, lips, tongue, and throat that may cause difficulty in breathing or swallowing.

What should I tell my doctor before taking JANUMET XR?
Before you take JANUMET XR, tell your doctor about all of your medical conditions, including if you:

- have or have had inflammation of your pancreas (pancreatitis).
- have kidney problems.
- have liver problems.
- have heart failure.
- drink alcohol very often, or drink a lot of alcohol in short-term "binge" drinking.
- are going to get an injection of dye or contrast agents for an x-ray procedure. JANUMET XR may need to be stopped for a short time. Talk to your doctor about when you should stop JANUMET XR and when you should start JANUMET XR again. See "What is the most important information I should know about JANUMET XR?".
- have low levels of vitamin B12 in your blood.
- are pregnant or plan to become pregnant. It is not known if JANUMET XR will harm your unborn baby. If you are pregnant, talk with your doctor about the best way to control your blood sugar while you are pregnant.
- are breastfeeding or plan to breastfeed. It is not known if JANUMET XR will pass into your breast milk. Talk with your doctor about the best way to feed your baby if you are taking JANUMET XR.
- are a woman who has not gone through menopause (premenopausal) who does not have periods regularly or at all. JANUMET XR can cause the release of an egg from an ovary in a woman (ovulation). This can increase your chance of getting pregnant. Tell your doctor right away if you become pregnant while taking JANUMET XR.

Tell your doctor about all the medicines you take, including prescription and over-the-counter medicines, vitamins, and herbal supplements. JANUMET XR may affect the way other medicines work and other medicines may affect how JANUMET XR works.
Know the medicines you take. Keep a list of your medicines and show it to your doctor and pharmacist when you get a new medicine.

How should I take JANUMET XR?

- Take JANUMET XR exactly as your doctor tells you. Your doctor will tell you how many JANUMET XR tablets to take and when you should take them.
- Your doctor may change your dose of JANUMET XR if needed.
- Your doctor may tell you to take JANUMET XR along with certain other diabetes medicines. Low blood sugar (hypoglycemia) can happen more often when JANUMET XR is taken with certain other diabetes medicines. See "What are the possible side effects of JANUMET XR?".
- Take JANUMET XR 1 time each day with a meal to help to lower your chance of having an upset stomach. It is better to take JANUMET XR with your evening meal.
- Take JANUMET XR tablets whole. Do not break, cut, crush, or chew JANUMET XR tablets before swallowing. If you cannot swallow JANUMET XR tablets whole, tell your doctor.
- You may see something that looks like the JANUMET XR tablet in your stool (bowel movement). If you see tablets in your stool several times, talk to your doctor. Do not stop taking JANUMET XR without talking to your doctor.
- Continue to take JANUMET XR as long as your doctor tells you.
- If you take too much JANUMET XR, call your doctor or local Poison Control Center right away.
- If you miss a dose, take it with food as soon as you remember. If you do not remember until it is time for your next dose, skip the missed dose and go back to your regular schedule. Do not take 2 doses of JANUMET XR at the same time.
- You may need to stop taking JANUMET XR for a short time. Call your doctor for instructions if you:
  - are dehydrated (have lost too much body fluid). Dehydration can occur if you are sick with severe vomiting, diarrhea or fever, or if you drink a lot less fluid than normal.
  - plan to have surgery.
  - are going to get an injection of dye or contrast agent for an x-ray procedure. See "What is the most important information I should know about JANUMET XR?" and "What should I tell my doctor before taking JANUMET XR?".
- When your body is under some types of stress, such as fever, trauma (such as a car accident), infection or surgery, the amount of diabetes medicine that you need may change. Tell your doctor right away if you have any of these problems and follow your doctor's instructions.
- Check your blood sugar as your doctor tells you to.
- Stay on your prescribed diet and exercise program while taking JANUMET XR.
- Talk to your doctor about how to prevent, recognize and manage low blood sugar (hypoglycemia), high blood sugar (hyperglycemia), and problems you have because of your diabetes.
- Your doctor will check your diabetes with regular blood tests, including your blood sugar levels and your hemoglobin A1C.
- Your doctor will do blood tests to check how well your kidneys are working before and during your treatment with JANUMET XR.

What are the possible side effects of JANUMET XR?
JANUMET XR may cause serious side effects, including:

- See "What is the most important information I should know about JANUMET XR?".
- Kidney problems, sometimes requiring dialysis.
- Low vitamin B12 (vitamin B12 deficiency). Using metformin for long periods of time may cause a decrease in the amount of vitamin B12 in your blood, especially if you have had low vitamin B12 blood levels before. Your doctor may do blood tests to check your vitamin B12 levels.
- Low blood sugar (hypoglycemia). If you take JANUMET XR with another medicine that can cause low blood sugar, such as a sulfonylurea or insulin, your risk of getting low blood sugar is higher. The dose of your sulfonylurea medicine or insulin may need to be lowered while you use JANUMET XR. Signs and symptoms of low blood sugar may include:

- headache
- drowsiness

- irritability
- hunger

- dizziness
- confusion

- sweating
- feeling jittery

- weakness
- fast heart beat

- Serious allergic reactions. If you have any symptoms of a serious allergic reaction, stop taking JANUMET XR and call your doctor right away or get emergency medical help. See "Who should not take JANUMET XR?". Your doctor may give you a medicine for your allergic reaction and prescribe a different medicine for your diabetes.
- Joint pain. Some people who take medicines called DPP-4 inhibitors, one of the medicines in JANUMET XR, may develop joint pain that can be severe. Call your doctor if you have severe joint pain.
- Skin reaction. Some people who take medicines called DPP-4 inhibitors, one of the medicines in JANUMET XR, may develop a skin reaction called bullous pemphigoid that can require treatment in a hospital. Tell your doctor right away if you develop blisters or the breakdown of the outer layer of your skin (erosion). Your doctor may tell you to stop taking JANUMET XR.

The most common side effects of JANUMET XR include:

- stuffy or runny nose and sore throat
- gas, upset stomach, indigestion
- headache

- upper respiratory infection
- weakness
- diarrhea

- low blood sugar (hypoglycemia) when used in combination with certain medicines, such as a sulfonylurea or insulin
- nausea and vomiting

Taking JANUMET XR with meals can help lessen the common stomach side effects of metformin that usually happen at the beginning of treatment. If you have unusual or sudden stomach problems, talk with your doctor. Stomach problems that start later during treatment may be a sign of something more serious.
JANUMET XR may have other side effects, including swelling of the hands or legs. Swelling of the hands and legs can happen if you take JANUMET XR in combination with rosiglitazone (Avandia). Rosiglitazone is another type of diabetes medicine.
Tell your doctor if you have any side effect that bothers you or does not go away.
These are not all the possible side effects of JANUMET XR. For more information, ask your doctor or pharmacist.
Call your doctor for medical advice about side effects. You may report side effects to FDA at 1-800-FDA-1088.

How should I store JANUMET XR?

- Store JANUMET XR at room temperature, between 68°F to 77°F (20°C to 25°C).
- Store in a dry place and keep the cap tightly closed.

Keep JANUMET XR and all medicines out of the reach of children.

General information about the safe and effective use of JANUMET XR.
Medicines are sometimes prescribed for purposes other than those listed in a Medication Guide. Do not use JANUMET XR for a condition for which it was not prescribed. Do not give JANUMET XR to other people, even if they have the same symptoms you have. It may harm them.
This Medication Guide summarizes the most important information about JANUMET XR. If you would like to know more information, talk with your doctor. You can ask your doctor or pharmacist for information about JANUMET XR that is written for health professionals.

What are the ingredients in JANUMET XR?
Active ingredients: sitagliptin and metformin hydrochloride extended-release
Inactive ingredients:

- All doses of JANUMET XR Tablets contain: povidone, hypromellose, colloidal silicon dioxide, sodium stearyl fumarate, propyl gallate, polyethylene glycol, and kaolin. Film coating contains hypromellose, hydroxypropyl cellulose, titanium dioxide, FD&C #2/Indigo Carmine Aluminum Lake and carnauba wax.
- In addition the JANUMET XR 50 mg/500 mg Tablets also contain: microcrystalline cellulose.
- In addition the JANUMET XR 50 mg/1000 mg Tablets film coating also contain: yellow iron oxide.

Dist. by: Merck Sharp & Dohme LLC
Rahway, NJ 07065, USA
For more information go to www.janumetxr.com or call 1-800-622-4477.
For patent information: www.msd.com/research/patent
The trademarks depicted herein are owned by their respective companies.
Copyright © 2012-2022 Merck & Co., Inc., Rahway, NJ, USA, and its affiliates.
All rights reserved.
usmg-mk0431a-xrt-2207r011

This Medication Guide has been approved by the U.S. Food and Drug Administration.

Revised: 07/2022

PRINCIPAL DISPLAY PANEL - 50 mg/500 mg Tablet Bottle Label

NDC 0006-0078-61

Janumet® XR
(sitagliptin and metformin HCl
extended-release) tablets

50 mg /500 mg

Dispense the accompanying Medication Guide
to each patient.

Each tablet contains 64.25 mg sitagliptin phosphate
(equivalent to 50 mg sitagliptin) and 500 mg
metformin hydrochloride
extended-release.

Rx only

60 Tablets

PRINCIPAL DISPLAY PANEL - 50 mg/1,000 mg Tablet Bottle Label

NDC 0006-0080-61

Janumet® XR
(sitagliptin and metformin HCl
extended-release) tablets

50 mg /1,000 mg

Dispense the accompanying Medication
Guide to each patient.

Each tablet contains 64.25 mg sitagliptin phosphate
(equivalent to 50 mg sitagliptin) and 1,000 mg
metformin hydrochloride
extended-release.

Rx only

60 Tablets

PRINCIPAL DISPLAY PANEL - 100 mg/1,000 mg Tablet Bottle Label

NDC 0006-0081-31

Janumet® XR
(sitagliptin and metformin HCl
extended-release) tablets

100 mg /1,000 mg

Dispense the accompanying Medication Guide
to each patient.

Each tablet contains 128.5 mg sitagliptin phosphate
(equivalent to 100 mg sitagliptin) and 1,000 mg
metformin hydrochloride
extended-release.

Rx only

30 Tablets